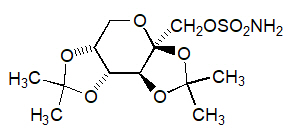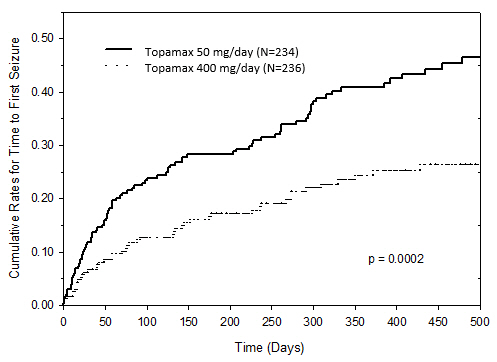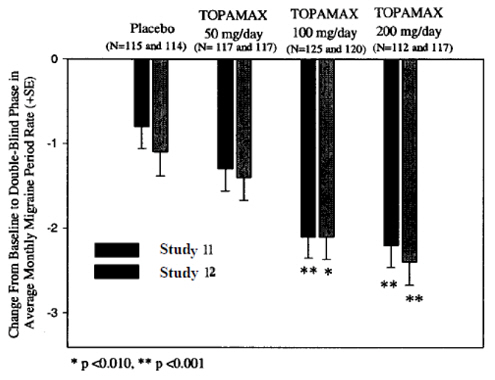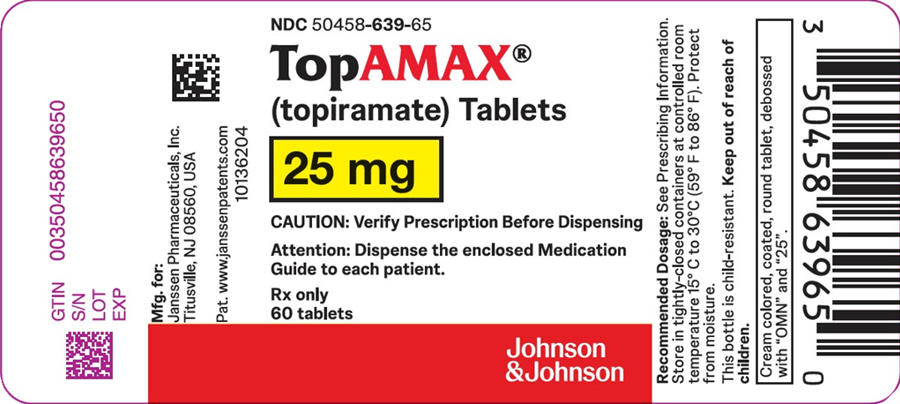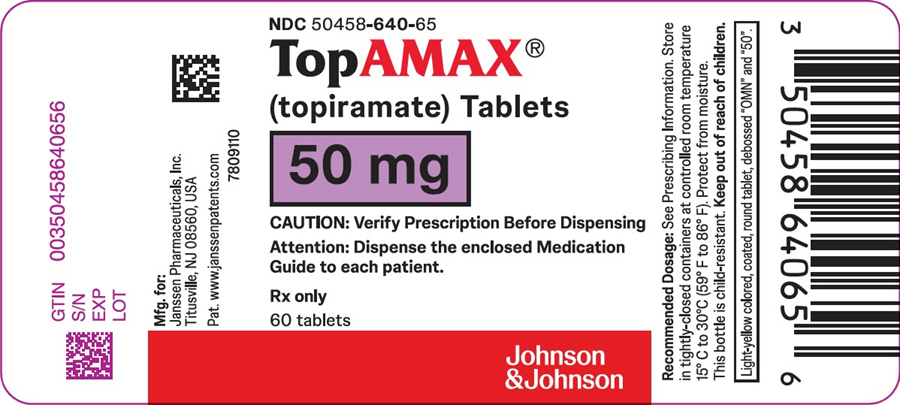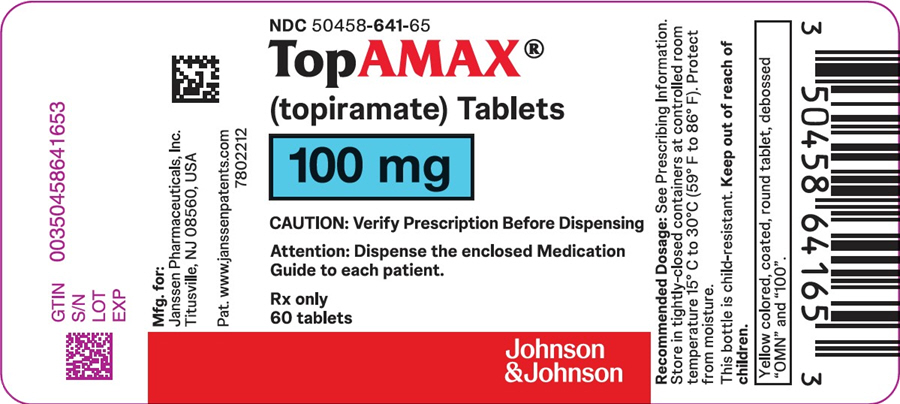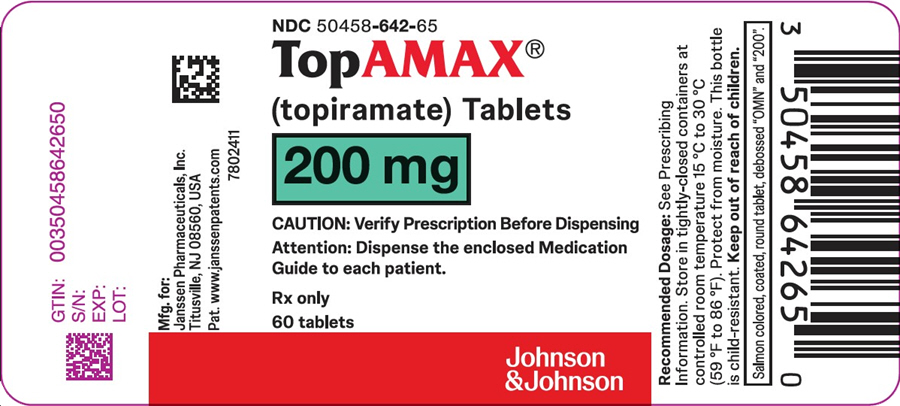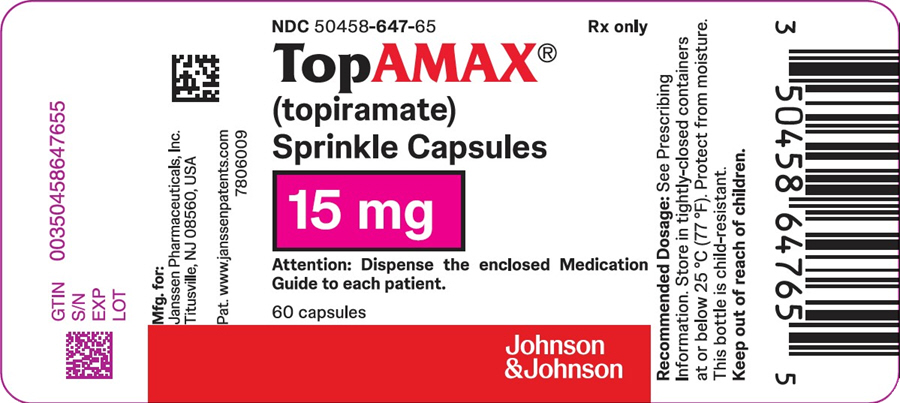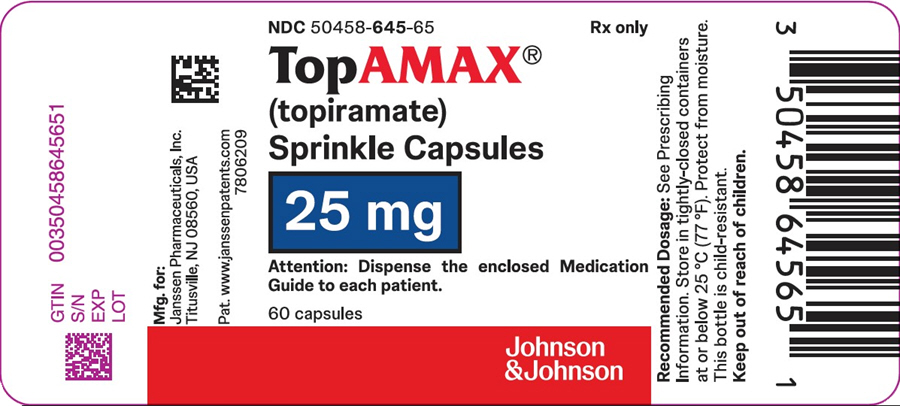 DRUG LABEL: Topamax
NDC: 50458-639 | Form: TABLET, COATED
Manufacturer: Janssen Pharmaceuticals, Inc.
Category: prescription | Type: HUMAN PRESCRIPTION DRUG LABEL
Date: 20260211

ACTIVE INGREDIENTS: TOPIRAMATE 25 mg/1 1
INACTIVE INGREDIENTS: LACTOSE MONOHYDRATE; MICROCRYSTALLINE CELLULOSE; SODIUM STARCH GLYCOLATE TYPE A POTATO; MAGNESIUM STEARATE; WATER; CARNAUBA WAX; HYPROMELLOSE, UNSPECIFIED; TITANIUM DIOXIDE; POLYETHYLENE GLYCOL, UNSPECIFIED; POLYSORBATE 80

HIGHLIGHTS OF PRESCRIBING INFORMATION

These highlights do not include all the information needed to use TOPAMAX®safely and effectively. See full prescribing information for TOPAMAX®
TOPAMAX®(topiramate) TABLETS, for oral use
TOPAMAX®(topiramate capsules) SPRINKLE CAPSULES, for oral use
Initial U.S. Approval: 1996

1 INDICATIONS AND USAGE

TOPAMAX is indicated for:

- Epilepsy: initial monotherapy for the treatment of partial-onset or primary generalized tonic-clonic seizures in patients 2 years of age and older (1.1); adjunctive therapy for the treatment of partial-onset seizures, primary generalized tonic-clonic seizures, or seizures associated with Lennox-Gastaut syndrome in patients 2 years of age and older (1.2)
- Preventive treatment of migraine in patients 12 years of age and older (1.3)

2 DOSAGE AND ADMINISTRATION

TOPAMAX initial dose, titration, and recommended maintenance dose varies by indication and age group. See Full Prescribing Information for recommended dosage, and dosing considerations in patients with renal impairment, geriatric patients, and patients undergoing hemodialysis (2.1, 2.2, 2.3, 2.4, 2.5, 2.6)

3 DOSAGE FORMS AND STRENGTHS

- Tablets: 25 mg, 50 mg, 100 mg, and 200 mg (3)
- Sprinkle Capsules: 15 mg and 25 mg (3)

4 CONTRAINDICATIONS

None (4)

5 WARNINGS AND PRECAUTIONS

- Acute myopia and secondary angle closure glaucoma: can lead to permanent visual loss; discontinue TOPAMAX as soon as possible (5.1)
- Visual field defects: consider discontinuation of TOPAMAX (5.2)
- Oligohidrosis and hyperthermia: monitor decreased sweating and increased body temperature, especially in pediatric patients (5.3)
- Metabolic acidosis: baseline and periodic measurement of serum bicarbonate is recommended; consider dose reduction or discontinuation of TOPAMAX if clinically appropriate (5.4)
- Suicidal behavior and ideation: antiepileptic drugs increase the risk of suicidal behavior or ideation (5.5)
- Cognitive/neuropsychiatric adverse reactions: use caution when operating machinery including cars; depression and mood problems may occur (5.6)
- Fetal Toxicity: use during pregnancy can cause major congenital malformations, including but not limited to cleft lip and/or palate, and being small for gestational age (5.7)
- Withdrawal of AEDs: withdraw TOPAMAX gradually (5.8)
- Decrease in Bone Mineral Density: has been shown to decrease bone mineral density and bone mineral content in pediatric patients (5.9)
- Negative effects on growth (height and weight): may slow height increase and weight gain; carefully monitor children receiving prolonged therapy (5.10)
- Serious skin reactions: If SJS or TEN is suspected, discontinue TOPAMAX (5.11)
- Hyperammonemia/encephalopathy: measure ammonia if encephalopathic symptoms occur (5.12)
- Kidney stones: avoid use with other carbonic anhydrase inhibitors, drugs causing metabolic acidosis, or in patients on a ketogenic diet (5.13)
- Hypothermia has been reported with and without hyperammonemia during topiramate treatment with concomitant valproic acid use (5.14)

6 ADVERSE REACTIONS

Epilepsy: Most common (≥10% more frequent than placebo or low-dose TOPAMAX) adverse reactions in adult and pediatric patients were: paresthesia, anorexia, weight loss, speech disorders/related speech problems, fatigue, dizziness, somnolence, nervousness, psychomotor slowing, abnormal vision and fever (6.1)

Migraine: Most common (≥5% more frequent than placebo) adverse reactions in adult and pediatric patients were: paresthesia, anorexia, weight loss, difficulty with memory, taste perversion, diarrhea, hypoesthesia, nausea, abdominal pain and upper respiratory tract infection (6.1)

To report SUSPECTED ADVERSE REACTIONS, contact Janssen Pharmaceuticals, Inc. at 1-800-526-7736 or FDA at 1-800-FDA-1088 or www.fda.gov/medwatch.

7 DRUG INTERACTIONS

- Contraceptives: decreased contraceptive efficacy and increased breakthrough bleeding, especially at doses greater than 200 mg/day (7.4)
- Monitor lithium levels if lithium is used with high-dose TOPAMAX (7.7)

FULL PRESCRIBING INFORMATION

1 INDICATIONS AND USAGE

1.1 Monotherapy Epilepsy

TOPAMAX is indicated as initial monotherapy for the treatment of partial-onset or primary generalized tonic-clonic seizures in patients 2 years of age and older.

1.2 Adjunctive Therapy Epilepsy

TOPAMAX is indicated as adjunctive therapy for the treatment of partial-onset seizures, primary generalized tonic-clonic seizures, and seizures associated with Lennox-Gastaut syndrome in patients 2 years of age and older.

1.3 Migraine

TOPAMAX is indicated for the preventive treatment of migraine in patients 12 years of age and older.

2 DOSAGE AND ADMINISTRATION

2.1 Dosing in Monotherapy Epilepsy

Adults and Pediatric Patients 10 Years of Age and Older

The recommended dose for TOPAMAX monotherapy in adults and pediatric patients 10 years of age and older is 400 mg/day in two divided doses. The dose should be achieved by titration according to the following schedule (Table 1):

Table 1: Monotherapy Titration Schedule for Adults and Pediatric Patients 10 years and older
 | Morning Dose | Evening Dose
Week 1 | 25 mg | 25 mg
Week 2 | 50 mg | 50 mg
Week 3 | 75 mg | 75 mg
Week 4 | 100 mg | 100 mg
Week 5 | 150 mg | 150 mg
Week 6 | 200 mg | 200 mg

Pediatric Patients 2 to 9 Years of Age

Dosing in patients 2 to 9 years of age is based on weight. During the titration period, the initial dose of TOPAMAX is 25 mg/day nightly for the first week. Based upon tolerability, the dosage can be increased to 50 mg/day (25 mg twice daily) in the second week. Dosage can be increased by 25–50 mg/day each subsequent week as tolerated. Titration to the minimum maintenance dose should be attempted over 5–7 weeks of the total titration period. Based upon tolerability and clinical response, additional titration to a higher dose (up to the maximum maintenance dose) can be attempted at 25–50 mg/day weekly increments. The total daily dose should not exceed the maximum maintenance dose for each range of body weight (Table 2).

Table 2: Monotherapy Target Total Daily Maintenance Dosing for Patients 2 to 9 Years of Age
Weight (kg) | Total Daily Dose (mg/day) [Administered in two equally divided doses] Minimum Maintenance Dose | Total Daily Dose (mg/day) Maximum Maintenance Dose
Up to 11 | 150 | 250
12 – 22 | 200 | 300
23 – 31 | 200 | 350
32 – 38 | 250 | 350
Greater than 38 | 250 | 400

2.2 Dosing in Adjunctive Therapy Epilepsy

Adults (17 Years of Age and Older)

The recommended total daily dose of TOPAMAX as adjunctive therapy in adults with partial onset seizures or Lennox-Gastaut Syndrome is 200 to 400 mg/day in two divided doses, and 400 mg/day in two divided doses as adjunctive treatment in adults with primary generalized tonic-clonic seizures. TOPAMAX should be initiated at 25 to 50 mg/day, followed by titration to an effective dose in increments of 25 to 50 mg/day every week. Titrating in increments of 25 mg/day every week may delay the time to reach an effective dose. Doses above 400 mg/day have not been shown to improve responses in adults with partial-onset seizures.

Pediatric Patients 2 to 16 Years of Age

The recommended total daily dose of TOPAMAX as adjunctive therapy for pediatric patients 2 to 16 years of age with partial-onset seizures, primary generalized tonic-clonic seizures, or seizures associated with Lennox-Gastaut syndrome is approximately 5 to 9 mg/kg/day in two divided doses. Titration should begin at 25 mg/day (or less, based on a range of 1 to 3 mg/kg/day) nightly for the first week. The dosage should then be increased at 1- or 2-week intervals by increments of 1 to 3 mg/kg/day (administered in two divided doses), to achieve optimal clinical response. Dose titration should be guided by clinical outcome. The total daily dose should not exceed 400 mg/day.

2.3 Dosing for the Preventive Treatment of Migraine

The recommended total daily dose of TOPAMAX as treatment for patients 12 years of age and older for the preventive treatment of migraine is 100 mg/day administered in two divided doses (Table 3). The recommended titration rate for TOPAMAX for the preventive treatment of migraine is as follows:

Table 3: Preventive Treatment of Migraine Titration Schedule for Patients 12 Years of Age and Older
 | Morning Dose | Evening Dose
Week 1 | None | 25 mg
Week 2 | 25 mg | 25 mg
Week 3 | 25 mg | 50 mg
Week 4 | 50 mg | 50 mg

Dose and titration rate should be guided by clinical outcome. If required, longer intervals between dose adjustments can be used.

2.4 Administration Information

TOPAMAX can be taken without regard to meals.

TOPAMAX Tablets

Because of the bitter taste, tablets should not be broken.

TOPAMAX Sprinkle Capsules

TOPAMAX Sprinkle Capsules may be swallowed whole or may be administered by carefully opening the capsule and sprinkling the entire contents on a small amount (teaspoon) of soft food. This drug/food mixture should be swallowed immediately and not chewed. It should not be stored for future use.

2.5 Dosing in Patients with Renal Impairment

In patients with renal impairment (creatinine clearance less than 70 mL/min/1.73 m^2), one-half of the usual adult dose of TOPAMAX is recommended [see Use in Specific Populations (8.5, 8.6), Clinical Pharmacology (12.3)] .

2.6 Dosing in Patients Undergoing Hemodialysis

To avoid rapid drops in topiramate plasma concentration during hemodialysis, a supplemental dose of TOPAMAX may be required. The actual adjustment should take into account 1) the duration of dialysis period, 2) the clearance rate of the dialysis system being used, and 3) the effective renal clearance of topiramate in the patient being dialyzed [see Use in Specific Populations (8.7), Clinical Pharmacology (12.3)] .

3 DOSAGE FORMS AND STRENGTHS

TOPAMAX Tablets are available as debossed, coated, round tablets in the following strengths and colors:

25 mg cream (debossed "OMN" on one side; "25" on the other)

50 mg light-yellow (debossed "OMN" on one side; "50" on the other)

100 mg yellow (debossed "OMN" on one side; "100" on the other)

200 mg salmon (debossed "OMN" on one side; "200" on the other)

TOPAMAX Sprinkle Capsules contain small, white to off-white spheres. The gelatin capsules are white and clear.

They are marked as follows:

15 mg capsule with "TOP" and "15 mg" on the side

25 mg capsule with "TOP" and "25 mg" on the side

4 CONTRAINDICATIONS

None.

5 WARNINGS AND PRECAUTIONS

5.1 Acute Myopia and Secondary Angle Closure Glaucoma Syndrome

A syndrome consisting of acute myopia associated with secondary angle closure glaucoma has been reported in patients receiving TOPAMAX. Symptoms include acute onset of decreased visual acuity and/or ocular pain. Ophthalmologic findings can include some or all of the following: myopia, mydriasis, anterior chamber shallowing, ocular hyperemia (redness), choroidal detachments, retinal pigment epithelial detachments, macular striae, and increased intraocular pressure. This syndrome may be associated with supraciliary effusion resulting in anterior displacement of the lens and iris, with secondary angle closure glaucoma. Symptoms typically occur within 1 month of initiating TOPAMAX therapy. In contrast to primary narrow angle glaucoma, which is rare under 40 years of age, secondary angle closure glaucoma associated with topiramate has been reported in pediatric patients as well as adults. The primary treatment to reverse symptoms is discontinuation of TOPAMAX as rapidly as possible, according to the judgment of the treating physician. Other measures, in conjunction with discontinuation of TOPAMAX, may be helpful.

Elevated intraocular pressure of any etiology, if left untreated, can lead to serious sequelae including permanent vision loss.

5.2 Visual Field Defects

Visual field defects (independent of elevated intraocular pressure) have been reported in clinical trials and in postmarketing experience in patients receiving topiramate. In clinical trials, most of these events were reversible after topiramate discontinuation. If visual problems occur at any time during topiramate treatment, consideration should be given to discontinuing the drug.

5.3 Oligohidrosis and Hyperthermia

Oligohidrosis (decreased sweating), infrequently resulting in hospitalization, has been reported in association with TOPAMAX use. Decreased sweating and an elevation in body temperature above normal characterized these cases. Some of the cases were reported after exposure to elevated environmental temperatures.

The majority of the reports have been in pediatric patients. Patients (especially pediatric patients) treated with TOPAMAX should be monitored closely for evidence of decreased sweating and increased body temperature, especially in hot weather. Caution should be used when TOPAMAX is given with other drugs that predispose patients to heat-related disorders; these drugs include, but are not limited to, other carbonic anhydrase inhibitors and drugs with anticholinergic activity.

5.4 Metabolic Acidosis

TOPAMAX can cause hyperchloremic, non-anion gap, metabolic acidosis (i.e., decreased serum bicarbonate below the normal reference range in the absence of chronic respiratory alkalosis). This metabolic acidosis is caused by renal bicarbonate loss due to carbonic anhydrase inhibition by TOPAMAX. TOPAMAX-induced metabolic acidosis can occur at any time during treatment. Bicarbonate decrements are usually mild-moderate (average decrease of 4 mEq/L at daily doses of 400 mg in adults and at approximately 6 mg/kg/day in pediatric patients); rarely, patients can experience severe decrements to values below 10 mEq/L. Conditions or therapies that predispose patients to acidosis (such as renal disease, severe respiratory disorders, status epilepticus, diarrhea, ketogenic diet, or specific drugs) may be additive to the bicarbonate lowering effects of TOPAMAX.

Metabolic acidosis was commonly observed in adult and pediatric patients treated with TOPAMAX in clinical trials. The incidence of decreased serum bicarbonate in pediatric trials, for adjunctive treatment of Lennox-Gastaut syndrome or refractory partial-onset seizures was as high as 67% for TOPAMAX (at approximately 6 mg/kg/day), and 10% for placebo. The incidence of a markedly abnormally low serum bicarbonate (i.e., absolute value < 17 mEq/L and ≥5 mEq/L decrease from pretreatment) in these trials was up to 11%, compared to ≤ 2% for placebo.

Manifestations of acute or chronic metabolic acidosis may include hyperventilation, nonspecific symptoms such as fatigue and anorexia, or more severe sequelae including cardiac arrhythmias or stupor. Chronic, untreated metabolic acidosis may increase the risk for nephrolithiasis or nephrocalcinosis, and may also result in osteomalacia (referred to as rickets in pediatric patients) and/or osteoporosis with an increased risk for fractures [see Warnings and Precautions (5.9, 5.13)] . A one-year, active-controlled study of pediatric patients treated with TOPAMAX demonstrated that TOPAMAX decreased lumbar spine bone mineral density and that this lumbar spine bone mineral density decrease was correlated (using change from baseline for lumbar spine Z score at final visit versus lowest post-treatment serum bicarbonate) with decreased serum bicarbonate, a reflection of metabolic acidosis [see Warnings and Precautions (5.9), Use in Specific Populations (8.4)] . Chronic metabolic acidosis in pediatric patients may also reduce growth rates, which may decrease the maximal height achieved. Long-term, open-label treatment of pediatric patients 1 to 24 months old with intractable partial epilepsy, for up to 1 year, showed reductions from baseline in length, weight, and head circumference compared to age and sex-matched normative data, although these patients with epilepsy are likely to have different growth rates than normal 1 to 24 month old pediatrics. Reductions in length and weight were correlated to the degree of acidosis [see Use in Specific Populations (8.4)] . TOPAMAX treatment that causes metabolic acidosis during pregnancy can possibly produce adverse effects on the fetus and might also cause metabolic acidosis in the neonate from possible transfer of topiramate to the fetus [see Warnings and Precautions (5.7), Use in Specific Populations (8.1)] .

Measurement of Serum Bicarbonate in Epilepsy and Migraine Patients

Measurement of baseline and periodic serum bicarbonate during topiramate treatment is recommended. If metabolic acidosis develops and persists, consideration should be given to reducing the dose or discontinuing TOPAMAX (using dose tapering). If the decision is made to continue patients on TOPAMAX in the face of persistent acidosis, alkali treatment should be considered.

5.5 Suicidal Behavior and Ideation

Antiepileptic drugs (AEDs), including TOPAMAX, increase the risk of suicidal thoughts or behavior in patients taking these drugs for any indication. Patients treated with any AED for any indication should be monitored for the emergence or worsening of depression, suicidal thoughts or behavior, and/or any unusual changes in mood or behavior.

Pooled analyses of 199 placebo-controlled clinical trials (mono- and adjunctive therapy) of 11 different AEDs showed that patients randomized to one of the AEDs had approximately twice the risk (adjusted Relative Risk 1.8, 95% CI:1.2, 2.7) of suicidal thinking or behavior compared to patients randomized to placebo. In these trials, which had a median treatment duration of 12 weeks, the estimated incidence rate of suicidal behavior or ideation among 27,863 AED-treated patients was 0.43%, compared to 0.24% among 16,029 placebo-treated patients, representing an increase of approximately one case of suicidal thinking or behavior for every 530 patients treated. There were four suicides in drug-treated patients in the trials and none in placebo-treated patients, but the number is too small to allow any conclusion about drug effect on suicide.

The increased risk of suicidal thoughts or behavior with AEDs was observed as early as one week after starting drug treatment with AEDs and persisted for the duration of treatment assessed. Because most trials included in the analysis did not extend beyond 24 weeks, the risk of suicidal thoughts or behavior beyond 24 weeks could not be assessed.

The risk of suicidal thoughts or behavior was generally consistent among drugs in the data analyzed. The finding of increased risk with AEDs of varying mechanisms of action and across a range of indications suggests that the risk applies to all AEDs used for any indication. The risk did not vary substantially by age (5 to 100 years) in the clinical trials analyzed.

Table 4 shows absolute and relative risk by indication for all evaluated AEDs.

Table 4: Risk by Indication for Antiepileptic Drugs in the Pooled Analysis
Indication | Placebo Patients with Events per 1000 Patients | Drug Patients with Events per 1000 Patients | Relative Risk: Incidence of Events in Drug Patients/Incidence in Placebo Patients | Risk Difference: Additional Drug Patients with Events per 1000 Patients
Epilepsy | 1.0 | 3.4 | 3.5 | 2.4
Psychiatric | 5.7 | 8.5 | 1.5 | 2.9
Other | 1.0 | 1.8 | 1.9 | 0.9
Total | 2.4 | 4.3 | 1.8 | 1.9

The relative risk for suicidal thoughts or behavior was higher in clinical trials for epilepsy than in clinical trials for psychiatric or other conditions, but the absolute risk differences were similar for the epilepsy and psychiatric indications.

Anyone considering prescribing TOPAMAX or any other AED must balance the risk of suicidal thoughts or behavior with the risk of untreated illness. Epilepsy and many other illnesses for which AEDs are prescribed are themselves associated with morbidity and mortality and an increased risk of suicidal thoughts and behavior. Should suicidal thoughts and behavior emerge during treatment, the prescriber needs to consider whether the emergence of these symptoms in any given patient may be related to the illness being treated.

5.6 Cognitive/Neuropsychiatric Adverse Reactions

TOPAMAX can cause cognitive/neuropsychiatric adverse reactions. The most frequent of these can be classified into three general categories: 1) Cognitive-related dysfunction (e.g., confusion, psychomotor slowing, difficulty with concentration/attention, difficulty with memory, speech or language problems, particularly word-finding difficulties); 2) Psychiatric/behavioral disturbances (e.g., depression or mood problems); and 3) Somnolence or fatigue.

Adult Patients

Cognitive-Related Dysfunction

Rapid titration rate and higher initial dose were associated with higher incidences of cognitive-related dysfunction.

In adult epilepsy adjunctive controlled trials, which used rapid titration (100–200 mg/day weekly increments), and target TOPAMAX doses of 200 mg – 1000 mg/day, 56% of patients in the 800 mg/day and 1000 mg/day dose groups experienced cognitive-related dysfunction compared to approximately 42% of patients in the 200–400 mg/day groups and 14% for placebo. In this rapid titration regimen, these dose-related adverse reactions began in the titration or in the maintenance phase, and in some patients these events began during titration and persisted into the maintenance phase.

In the monotherapy epilepsy controlled trial, the proportion of patients who experienced one or more cognitive-related adverse reactions was 19% for TOPAMAX 50 mg/day and 26% for 400 mg/day.

In the 6-month controlled trials for the preventive treatment of migraine, which used a slower titration regimen (25 mg/day weekly increments), the proportion of patients who experienced one or more cognitive-related adverse reactions was 19% for TOPAMAX 50 mg/day, 22% for 100 mg/day (the recommended dose), 28% for 200 mg/day, and 10% for placebo. Cognitive adverse reactions most commonly developed during titration and sometimes persisted after completion of titration.

Psychiatric/Behavioral Disturbances

Psychiatric/behavioral disturbances (e.g., depression, mood) were dose-related for both the adjunctive epilepsy and migraine populations [see Warnings and Precautions (5.5)].

Somnolence/Fatigue

Somnolence and fatigue were the adverse reactions most frequently reported during clinical trials of TOPAMAX for adjunctive epilepsy. For the adjunctive epilepsy population, the incidence of fatigue, appeared dose related. For the monotherapy epilepsy population, the incidence of somnolence was dose-related. For the migraine population, the incidences of both fatigue and somnolence were dose-related and more common in the titration phase.

Pediatric Patients

In pediatric epilepsy trials (adjunctive and monotherapy), the incidence of cognitive/neuropsychiatric adverse reactions was generally lower than that observed in adults. These reactions included psychomotor slowing, difficulty with concentration/attention, speech disorders/related speech problems, and language problems. The most frequently reported cognitive/neuropsychiatric reactions in pediatric epilepsy patients during adjunctive therapy double-blind studies were somnolence and fatigue. The most frequently reported cognitive/neuropsychiatric reactions in pediatric epilepsy patients in the 50 mg/day and 400 mg/day groups during the monotherapy double-blind study were headache, dizziness, anorexia, and somnolence.

In pediatric migraine patients, the incidence of cognitive/neuropsychiatric adverse reactions was increased in TOPAMAX-treated patients compared to placebo.

The risk for cognitive/neuropsychiatric adverse reactions was dose-dependent, and was greatest at the highest dose (200 mg). This risk for cognitive/neuropsychiatric adverse reactions was also greater in younger patients (6 to 11 years of age) than in older patients (12 to 17 years of age).

The most common cognitive/neuropsychiatric adverse reaction in these trials was difficulty with concentration/attention. Cognitive adverse reactions most commonly developed during titration and sometimes persisted for various durations after completion of titration.

The Cambridge Neuropsychological Test Automated Battery (CANTAB) was administered to adolescents (12 to 17 years) to assess the effects of topiramate on cognitive function at baseline and at the end of the Study 13 [see Clinical Studies (14.3)] . Mean change from baseline in certain CANTAB tests suggests that topiramate treatment may result in psychomotor slowing and decreased verbal fluency.

5.7 Fetal Toxicity

TOPAMAX can cause fetal harm when administered to a pregnant woman. Data from pregnancy registries indicate that infants exposed to topiramate in uterohave an increased risk of major congenital malformations, including but not limited to cleft lip and/or cleft palate (oral clefts), and of being small for gestational age (SGA). When multiple species of pregnant animals received topiramate at clinically relevant doses, structural malformations, including craniofacial defects, and reduced fetal weights occurred in offspring [see Use in Specific Populations (8.1)] .

Consider the benefits and the risks of TOPAMAX when administering this drug in women of childbearing potential, particularly when TOPAMAX is considered for a condition not usually associated with permanent injury or death [see Use in Specific Populations (8.1), Patient Counseling Information (17)] . TOPAMAX should be used during pregnancy only if the potential benefit outweighs the potential risk. If this drug is used during pregnancy, or if the patient becomes pregnant while taking this drug, the patient should be apprised of the potential hazard to a fetus [see Use in Specific Populations (8.1)] .

5.8 Withdrawal of Antiepileptic Drugs

In patients with or without a history of seizures or epilepsy, antiepileptic drugs, including TOPAMAX, should be gradually withdrawn to minimize the potential for seizures or increased seizure frequency [see Clinical Studies (14)] . In situations where rapid withdrawal of TOPAMAX is medically required, appropriate monitoring is recommended.

5.9 Decrease in Bone Mineral Density

Results of a one-year active-controlled study in pediatric patients (N=63) demonstrated negative effects of TOPAMAX monotherapy on bone mineral acquisition via statistically significant decreases in bone mineral density (BMD) measured in lumbar spine and in total body less head [see Use in Specific Populations (8.4)] . Twenty-one percent of TOPAMAX-treated patients experienced clinically important reductions in BMD (Z score change from baseline of –0.5 or greater) compared to 0 patients in the control group. Although decreases in BMD occurred across all pediatric age subgroups, patients 6 to 9 years of age were most commonly affected. The sample size and study duration were too small to determine if fracture risk is increased. Decreased BMD in the lumbar spine was correlated with decreased serum bicarbonate, which commonly occurs with TOPAMAX treatment and reflects metabolic acidosis, a known cause of increased bone resorption [see Warnings and Precautions (5.4)] . Although small decreases in some markers of bone metabolism (e.g., serum alkaline phosphatase, calcium, phosphorus, and 1,25-dihydroxyvitamin D) occurred in TOPAMAX-treated patients, more significant decreases in serum parathyroid hormone and 25-hydroxyvitamin D, hormones involved in bone metabolism, were observed, along with an increased excretion of urinary calcium .

5.10 Negative Effects on Growth (Height and Weight)

Results of a one-year active-controlled study of pediatric patients (N=63) demonstrated negative effects of TOPAMAX monotherapy on growth (i.e., height and weight) [see Use in Specific Populations (8.4)] . Although continued growth was observed in both treatment groups, the TOPAMAX group showed statistically significant reductions in mean annual change from baseline in body weight compared to the control group. A similar trend of attenuation in height velocity and height change from baseline was also observed in the TOPAMAX group compared to the control group. Negative effects on weight and height were seen across all TOPAMAX age subgroups. Growth (height and weight) of children receiving prolonged TOPAMAX therapy should be carefully monitored.

5.11 Serious Skin Reactions

Serious skin reactions (Stevens-Johnson Syndrome [SJS] and Toxic Epidermal Necrolysis [TEN]) have been reported in patients receiving topiramate. TOPAMAX should be discontinued at the first sign of a rash, unless the rash is clearly not drug-related. If signs or symptoms suggest SJS/TEN, use of this drug should not be resumed and alternative therapy should be considered. Inform patients about the signs of serious skin reactions.

5.12 Hyperammonemia and Encephalopathy (Without and With Concomitant Valproic Acid Use)

Topiramate treatment can cause hyperammonemia with or without encephalopathy [see Adverse Reactions (6.2)] . The risk for hyperammonemia with topiramate appears dose-related. Hyperammonemia has been reported more frequently when topiramate is used concomitantly with valproic acid. Postmarketing cases of hyperammonemia with or without encephalopathy have been reported with topiramate and valproic acid in patients who previously tolerated either drug alone [see Drug Interactions (7.1)] .

Clinical symptoms of hyperammonemic encephalopathy often include acute alterations in level of consciousness and/or cognitive function with lethargy and/or vomiting. In most cases, hyperammonemic encephalopathy abated with discontinuation of treatment.

The incidence of hyperammonemia in pediatric patients 12 to 17 years of age in the preventive treatment of migraine trials was 26% in patients taking TOPAMAX monotherapy at 100 mg/day, and 14% in patients taking TOPAMAX at 50 mg/day, compared to 9% in patients taking placebo. There was also an increased incidence of markedly increased hyperammonemia at the 100 mg dose.

Dose-related hyperammonemia was also seen in pediatric patients 1 to 24 months of age treated with TOPAMAX and concomitant valproic acid for partial-onset epilepsy and this was not due to a pharmacokinetic interaction.

In some patients, hyperammonemia can be asymptomatic.

Monitoring for Hyperammonemia

Patients with inborn errors of metabolism or reduced hepatic mitochondrial activity may be at an increased risk for hyperammonemia with or without encephalopathy. Although not studied, topiramate treatment or an interaction of concomitant topiramate and valproic acid treatment may exacerbate existing defects or unmask deficiencies in susceptible persons.

In patients who develop unexplained lethargy, vomiting or changes in mental status associated with any topiramate treatment, hyperammonemic encephalopathy should be considered and an ammonia level should be measured.

5.13 Kidney Stones

TOPAMAX increases the risk of kidney stones. During adjunctive epilepsy trials, the risk for kidney stones in TOPAMAX-treated adults was 1.5%, an incidence about 2 to 4 times greater than expected in a similar, untreated population. As in the general population, the incidence of stone formation among TOPAMAX-treated patients was higher in men. Kidney stones have also been reported in pediatric patients taking TOPAMAX for epilepsy or migraine. During long-term (up to 1 year) TOPAMAX treatment in an open-label extension study of 284 pediatric patients 1–24 months old with epilepsy, 7% developed kidney or bladder stones. TOPAMAX is not approved for treatment of epilepsy in pediatric patients less than 2 years old [see Use in Specific Populations (8.4)].

TOPAMAX is a carbonic anhydrase inhibitor. Carbonic anhydrase inhibitors can promote stone formation by reducing urinary citrate excretion and by increasing urinary pH [see Warnings and Precautions (5.4)] . The concomitant use of TOPAMAX with any other drug producing metabolic acidosis, or potentially in patients on a ketogenic diet, may create a physiological environment that increases the risk of kidney stone formation, and should therefore be avoided.

Increased fluid intake increases the urinary output, lowering the concentration of substances involved in stone formation. Hydration is recommended to reduce new stone formation.

An increase in urinary calcium and a marked decrease in urinary citrate was observed in TOPAMAX-treated pediatric patients in a one-year active-controlled study [see Use in Specific Populations (8.4)] . This increased ratio of urinary calcium/citrate increases the risk of kidney stones and/or nephrocalcinosis.

5.14 Hypothermia with Concomitant Valproic Acid Use

Hypothermia, defined as a drop in body core temperature to <35 °C (95 °F), has been reported in association with topiramate use with concomitant valproic acid both in conjunction with hyperammonemia and in the absence of hyperammonemia. This adverse reaction in patients using concomitant topiramate and valproate can occur after starting topiramate treatment or after increasing the daily dose of topiramate [see Drug Interactions (7.1)] . Consideration should be given to stopping TOPAMAX or valproate in patients who develop hypothermia, which may be manifested by a variety of clinical abnormalities including lethargy, confusion, coma, and significant alterations in other major organ systems such as the cardiovascular and respiratory systems. Clinical management and assessment should include examination of blood ammonia levels.

6 ADVERSE REACTIONS

The following serious adverse reactions are discussed in more detail in other sections of the labeling:

- Acute Myopia and Secondary Angle Closure Glaucoma [see Warnings and Precautions (5.1)]
- Visual Field Defects [see Warnings and Precautions (5.2)]
- Oligohidrosis and Hyperthermia [see Warnings and Precautions (5.3)]
- Metabolic Acidosis [see Warnings and Precautions (5.4)]
- Suicidal Behavior and Ideation [see Warnings and Precautions (5.5)]
- Cognitive/Neuropsychiatric Adverse Reactions [see Warnings and Precautions (5.6)]
- Decrease of Bone Mineral Density [see Warnings and Precautions (5.9)]
- Negative Effects on Growth (Height and Weight) [see Warnings and Precautions (5.10)]
- Serious Skin Reactions [see Warnings and Precautions (5.11)]
- Hyperammonemia and Encephalopathy (Without and With Concomitant Valproic Acid [VPA] Use) [see Warnings and Precautions (5.12)]
- Kidney Stones [see Warnings and Precautions (5.13)]
- Hypothermia with Concomitant Valproic Acid (VPA) Use [see Warnings and Precautions (5.14)]

The data described in the following sections were obtained using TOPAMAX Tablets.

6.1 Clinical Trials Experience

Because clinical trials are conducted under widely varying conditions, the incidence of adverse reactions observed in the clinical trials of a drug cannot be directly compared to the incidence of adverse reactions in the clinical trials of another drug, and may not reflect the incidence of adverse reactions observed in practice.

Monotherapy Epilepsy

Adults 16 Years of Age and Older

The most common adverse reactions in the controlled clinical trial (Study 1) that occurred in adults in the 400 mg/day TOPAMAX group and at an incidence higher (≥ 10%) than in the 50 mg/day group were: paresthesia, weight loss and anorexia (see Table 5).

Approximately 21% of the 159 adult patients in the 400 mg/day group who received TOPAMAX as monotherapy in Study 1 discontinued therapy due to adverse reactions. The most common (≥ 2% more frequent than low-dose 50 mg/day TOPAMAX) adverse reactions causing discontinuation were difficulty with memory, fatigue, asthenia, insomnia, somnolence, and paresthesia.

Pediatric Patients 6 to 15 Years of Age

The most common adverse reactions in the controlled clinical trial (Study 1) that occurred in pediatric patients in the 400 mg/day TOPAMAX group and at an incidence higher (≥10%) than in the 50 mg/day group were fever and weight loss (see Table 5).

Approximately 14% of the 77 pediatric patients in the 400 mg/day group who received TOPAMAX as monotherapy in the controlled clinical trial discontinued therapy due to adverse reactions. The most common (≥2% more frequent than low-dose 50 mg/day TOPAMAX) adverse reactions resulting in discontinuation were difficulty with concentration/attention, fever, flushing, and confusion.

Table 5 presents the incidence of adverse reactions occurring in at least 3% of adult and pediatric patients treated with 400 mg/day TOPAMAX and occurring with greater incidence than 50 mg/day TOPAMAX.

Table 5: Adverse Reactions in the High Dose Group As Compared to the Low Dose Group, in Monotherapy Epilepsy Trial (Study 1) in Adult and Pediatric Patients
 | Age Group
 | Pediatric (6 to 15 Years) |  | Adult (Age ≥16 Years)
 | TOPAMAX Daily Dosage Group (mg/day)
 | 50 | 400 | 50 | 400
Body System | (N=74) | (N=77) | (N=160) | (N=159)
Adverse Reaction | % | % | % | %
Body as a Whole - General Disorders
Asthenia | 0 | 3 | 4 | 6
Fever | 1 | 12
Leg pain |  |  | 2 | 3
Central & Peripheral Nervous System Disorders
Paresthesia | 3 | 12 | 21 | 40
Dizziness |  |  | 13 | 14
Ataxia |  |  | 3 | 4
Hypoesthesia |  |  | 4 | 5
Hypertonia |  |  | 0 | 3
Involuntary muscle contractions | 0 | 3
Vertigo | 0 | 3
Gastro-Intestinal System Disorders
Constipation |  |  | 1 | 4
Diarrhea | 8 | 9
Gastritis |  |  | 0 | 3
Dry mouth |  |  | 1 | 3
Liver and Biliary System Disorders
Increase in Gamma-GT |  |  | 1 | 3
Metabolic and Nutritional Disorders
Weight loss | 7 | 17 | 6 | 17
Platelet, Bleeding & Clotting Disorders
Epistaxis | 0 | 4
Psychiatric Disorders
Anorexia |  |  | 4 | 14
Anxiety |  |  | 4 | 6
Cognitive problems | 1 | 6 | 1 | 4
Confusion | 0 | 3
Depression | 0 | 3 | 7 | 9
Difficulty with concentration or attention | 7 | 10 | 7 | 8
Difficulty with memory | 1 | 3 | 6 | 11
Insomnia |  |  | 8 | 9
Decrease in libido |  |  | 0 | 3
Mood problems | 1 | 8 | 2 | 5
Personality disorder (behavior problems) | 0 | 3
Psychomotor slowing |  |  | 3 | 5
Somnolence |  |  | 10 | 15
Red Blood Cell Disorders
Anemia | 1 | 3
Reproductive Disorders, Female
Intermenstrual bleeding | 0 | 3
Vaginal hemorrhage |  |  | 0 | 3
Resistance Mechanism Disorders
Infection | 3 | 8 | 2 | 3
Viral infection | 3 | 6 | 6 | 8
Respiratory System Disorders
Bronchitis | 1 | 5 | 3 | 4
Upper respiratory tract infection | 16 | 18
Rhinitis | 5 | 6 | 2 | 4
Sinusitis | 1 | 4
Skin and Appendages Disorders
Alopecia | 1 | 4 | 3 | 4
Pruritus |  |  | 1 | 4
Rash | 3 | 4 | 1 | 4
Acne |  |  | 2 | 3
Special Senses Other, Disorders
Taste perversion |  |  | 3 | 5
Urinary System Disorders
Cystitis |  |  | 1 | 3
Micturition frequency | 0 | 3
Renal calculus |  |  | 0 | 3
Urinary incontinence | 1 | 3
Vascular (Extracardiac) Disorders
Flushing | 0 | 5

Adjunctive Therapy Epilepsy

Adults 16 Years of Age and Older

In pooled controlled clinical trials in adults with partial-onset seizures, primary generalized tonic-clonic seizures, or Lennox-Gastaut syndrome, 183 patients received adjunctive therapy with TOPAMAX at dosages of 200 to 400 mg/day (recommended dosage range) and 291 patients received placebo. Patients in these trials were receiving 1 to 2 concomitant antiepileptic drugs in addition to TOPAMAX or placebo.

The most common adverse reactions in the controlled clinical trial that occurred in adult patients in the 200–400 mg/day TOPAMAX group with an incidence higher (≥ 10%) than in the placebo group were: dizziness, speech disorders/related speech problems, somnolence, nervousness, psychomotor slowing, and vision abnormal (Table 6).

Table 6 presents the incidence of adverse reactions occurring in at least 3% of adult patients treated with 200 to 400 mg/day TOPAMAX and was greater than placebo incidence. The incidence of some adverse reactions (e.g., fatigue, dizziness, paresthesia, language problems, psychomotor slowing, depression, difficulty with concentration/attention, mood problems) was dose-related and much greater at higher than recommended TOPAMAX dosing (i.e., 600 mg – 1000 mg daily) compared to the incidence of these adverse reactions at the recommended dosing (200 mg to 400 mg daily) range.

Table 6: Most Common Adverse Reactions in Pooled Placebo-Controlled, Adjunctive Epilepsy Trials in Adults [Patients in these adjunctive trials were receiving 1 to 2 concomitant antiepileptic drugs in addition to TOPAMAX or placebo.]
Body System Adverse Reaction | Placebo (N=291) | TOPAMAX Dosage (mg/day) 200–400 (N=183)
Body as a Whole-General Disorders
Fatigue | 13 | 15
Asthenia | 1 | 6
Back pain | 4 | 5
Chest pain | 3 | 4
Influenza-like symptoms | 2 | 3
Central & Peripheral Nervous System Disorders
Dizziness | 15 | 25
Ataxia | 7 | 16
Speech disorders/Related speech problems | 2 | 13
Paresthesia | 4 | 11
Nystagmus | 7 | 10
Tremor | 6 | 9
Language problems | 1 | 6
Coordination abnormal | 2 | 4
Gait abnormal | 1 | 3
Gastro-Intestinal System Disorders
Nausea | 8 | 10
Dyspepsia | 6 | 7
Abdominal pain | 4 | 6
Constipation | 2 | 4
Metabolic and Nutritional Disorders
Weight loss | 3 | 9
Psychiatric Disorders
Somnolence | 12 | 29
Nervousness | 6 | 16
Psychomotor slowing | 2 | 13
Difficulty with memory | 3 | 12
Confusion | 5 | 11
Anorexia | 4 | 10
Difficulty with concentration/attention | 2 | 6
Mood problems | 2 | 4
Agitation | 2 | 3
Aggressive reaction | 2 | 3
Emotional lability | 1 | 3
Cognitive problems | 1 | 3
Reproductive Disorders
Breast pain | 2 | 4
Respiratory System Disorders
Rhinitis | 6 | 7
Pharyngitis | 2 | 6
Sinusitis | 4 | 5
Vision Disorders
Vision abnormal | 2 | 13
Diplopia | 5 | 10

In controlled clinical trials in adults, 11% of patients receiving TOPAMAX 200 to 400 mg/day as adjunctive therapy discontinued due to adverse reactions. This rate appeared to increase at dosages above 400 mg/day. Adverse reactions associated with discontinuing TOPAMAX included somnolence, dizziness, anxiety, difficulty with concentration or attention, fatigue and paresthesia.

Pediatric Patients 2 to 15 Years of Age

In pooled, controlled clinical trials in pediatric patients (2 to 15 years of age) with partial-onset seizures, primary generalized tonic-clonic seizures, or Lennox-Gastaut syndrome, 98 patients received adjunctive therapy with TOPAMAX at dosages of 5 to 9 mg/kg/day (recommended dose range) and 101 patients received placebo.

The most common adverse reactions in the controlled clinical trial that occurred in pediatric patients in the 5 mg to 9 mg/kg/day TOPAMAX group with an incidence higher (≥ 10%) than in the placebo group were: fatigue and somnolence (Table 7).

Table 7 presents the incidence of adverse reactions that occurred in at least 3% of pediatric patients 2 to 15 years of age receiving 5 mg to 9 mg/kg/day (recommended dose range) of TOPAMAX and was greater than placebo incidence.

Table 7: Adverse Reactions in Pooled Placebo-Controlled, Adjunctive Epilepsy Trials in Pediatric Patients 2 to 15 Years of Age [Patients in these adjunctive trials were receiving 1 to 2 concomitant antiepileptic drugs in addition to TOPAMAX or placebo.] , [Values represent the percentage of patients reporting a given adverse reaction. Patients may have reported more than one adverse reaction during the study and can be included in more than one adverse reaction category.]
Body System/ Adverse Reaction | Placebo (N=101) % | TOPAMAX (N=98) %
Body as a Whole - General Disorders
Fatigue | 5 | 16
Injury | 13 | 14
Central & Peripheral Nervous System Disorders
Gait abnormal | 5 | 8
Ataxia | 2 | 6
Hyperkinesia | 4 | 5
Dizziness | 2 | 4
Speech disorders/Related speech problems | 2 | 4
Gastro-Intestinal System Disorders
Nausea | 5 | 6
Saliva increased | 4 | 6
Constipation | 4 | 5
Gastroenteritis | 2 | 3
Metabolic and Nutritional Disorders
Weight loss | 1 | 9
Platelet, Bleeding, & Clotting Disorders
Purpura | 4 | 8
Epistaxis | 1 | 4
Psychiatric Disorders
Somnolence | 16 | 26
Anorexia | 15 | 24
Nervousness | 7 | 14
Personality disorder (behavior problems) | 9 | 11
Difficulty with concentration/attention | 2 | 10
Aggressive reaction | 4 | 9
Insomnia | 7 | 8
Difficulty with memory | 0 | 5
Confusion | 3 | 4
Psychomotor slowing | 2 | 3
Resistance Mechanism Disorders
Infection viral | 3 | 7
Respiratory System Disorders
Pneumonia | 1 | 5
Skin and Appendages Disorders
Skin disorder | 2 | 3
Urinary System Disorders
Urinary incontinence | 2 | 4

None of the pediatric patients who received TOPAMAX adjunctive therapy at 5 to 9 mg/kg/day in controlled clinical trials discontinued due to adverse reactions.

Migraine

Adults

In the four multicenter, randomized, double-blind, placebo-controlled, parallel group migraine clinical trials for the preventive treatment of migraine (which included 35 pediatric patients 12 to 15 years of age), most adverse reactions occurred more frequently during the titration period than during the maintenance period.

The most common adverse reactions with TOPAMAX 100 mg in the clinical trials for the preventive treatment of migraine of predominantly adults that were seen at an incidence higher (≥ 5%) than in the placebo group were: paresthesia, anorexia, weight loss, taste perversion, diarrhea, difficulty with memory, hypoesthesia, and nausea (see Table 8).

Table 8 includes those adverse reactions that occurred in the placebo-controlled trials where the incidence in any TOPAMAX treatment group was at least 3% and was greater than that for placebo patients. The incidence of some adverse reactions (e.g., fatigue, dizziness, somnolence, difficulty with memory, difficulty with concentration/attention) was dose-related and greater at higher than recommended TOPAMAX dosing (200 mg daily) compared to the incidence of these adverse reactions at the recommended dosing (100 mg daily).

Table 8: Adverse Reactions in Pooled, Placebo-Controlled, Migraine Trials in Adults [Includes 35 adolescent patients age 12 to 15 years.] , [Values represent the percentage of patients reporting a given adverse reaction. Patients may have reported more than one adverse reaction during the study and can be included in more than one adverse reaction category.]
 |  | TOPAMAX Dosage (mg/day)
Body System/ Adverse Reaction | Placebo (N=445) % | 50 (N=235) % | 100 (N=386) %
Body as a Whole-General Disorders
Fatigue | 11 | 14 | 15
Injury | 7 | 9 | 6
Central & Peripheral Nervous System Disorders
Paresthesia | 6 | 35 | 51
Dizziness | 10 | 8 | 9
Hypoesthesia | 2 | 6 | 7
Language problems | 2 | 7 | 6
Gastro-Intestinal System Disorders
Nausea | 8 | 9 | 13
Diarrhea | 4 | 9 | 11
Abdominal pain | 5 | 6 | 6
Dyspepsia | 3 | 4 | 5
Dry mouth | 2 | 2 | 3
Gastroenteritis | 1 | 3 | 3
Metabolic and Nutritional Disorders
Weight loss | 1 | 6 | 9
Musculoskeletal System Disorders
Arthralgia | 2 | 7 | 3
Psychiatric Disorders
Anorexia | 6 | 9 | 15
Somnolence | 5 | 8 | 7
Difficulty with memory | 2 | 7 | 7
Insomnia | 5 | 6 | 7
Difficulty with concentration/attention | 2 | 3 | 6
Mood problems | 2 | 3 | 6
Anxiety | 3 | 4 | 5
Depression | 4 | 3 | 4
Nervousness | 2 | 4 | 4
Confusion | 2 | 2 | 3
Psychomotor slowing | 1 | 3 | 2
Reproductive Disorders, Female
Menstrual disorder | 2 | 3 | 2
Reproductive Disorders, Male
Ejaculation premature | 0 | 3 | 0
Resistance Mechanism Disorders
Viral infection | 3 | 4 | 4
Respiratory System Disorders
Upper respiratory tract infection | 12 | 13 | 14
Sinusitis | 6 | 10 | 6
Pharyngitis | 4 | 5 | 6
Coughing | 2 | 2 | 4
Bronchitis | 2 | 3 | 3
Dyspnea | 2 | 1 | 3
Skin and Appendages Disorders
Pruritus | 2 | 4 | 2
Special Sense Other, Disorders
Taste perversion | 1 | 15 | 8
Urinary System Disorders
Urinary tract infection | 2 | 4 | 2
Vision Disorders
Blurred vision [Blurred vision was the most common term considered as vision abnormal. Blurred vision was an included term that accounted for >50% of reactions coded as vision abnormal, a preferred term.] | 2 | 4 | 2

Of the 1,135 patients exposed to TOPAMAX in the adult placebo-controlled studies, 25% of TOPAMAX-treated patients discontinued due to adverse reactions, compared to 10% of the 445 placebo-treated patients. The adverse reactions associated with discontinuing therapy in the TOPAMAX-treated patients included paresthesia (7%), fatigue (4%), nausea (4%), difficulty with concentration/attention (3%), insomnia (3%), anorexia (2%), and dizziness (2%).

Patients treated with TOPAMAX experienced mean percent reductions in body weight that were dose-dependent. This change was not seen in the placebo group. Mean changes of 0%, -2%, -3%, and -4% were seen for the placebo group, TOPAMAX 50, 100, and 200 mg groups, respectively.

Pediatric Patients 12 to 17 Years of Age

In five, randomized, double-blind, placebo-controlled, parallel group clinical trials for the preventive treatment of migraine, most adverse reactions occurred more frequently during the titration period than during the maintenance period. Among adverse reactions with onset during titration, approximately half persisted into the maintenance period.

In four, fixed-dose, double-blind clinical trials for the preventive treatment of migraine in TOPAMAX-treated pediatric patients 12 to 17 years of age, the most common adverse reactions with TOPAMAX 100 mg that were seen at an incidence higher (≥5%) than in the placebo group were: paresthesia, upper respiratory tract infection, anorexia, and abdominal pain (see Table 9). Table 9 shows adverse reactions from the pediatric trial (Study 13 [see Clinical Studies (14.3)]) in which 103 pediatric patients were treated with placebo or 50 mg or 100 mg of TOPAMAX, and three predominantly adult trials in which 49 pediatric patients (12 to 17 years of age) were treated with placebo or 50 mg, 100 mg or 200 mg of TOPAMAX. Table 9 also shows adverse reactions in pediatric patients in the controlled migraine trials when the incidence in a TOPAMAX dose group was at least 5% or higher and greater than the incidence of placebo. Many adverse reactions shown in Table 9 indicate a dose-dependent relationship. The incidence of some adverse reactions (e.g., allergy, fatigue, headache, anorexia, insomnia, somnolence, and viral infection) was dose-related and greater at higher than recommended TOPAMAX dosing (200 mg daily) compared to the incidence of these adverse reactions at the recommended dosing (100 mg daily).

Table 9: Adverse Reactions in Pooled Double-Blind Studies for the Preventive Treatment of Migraine in Pediatric Patients 12 to 17 Years of Age [35 adolescent patients aged 12 to <16 years were also included in adverse reaction assessment for adults (Tables 11 and 12)] , [Incidence is based on the number of subjects experiencing at least 1 adverse event, not the number of events.] , [Included studies MIG-3006, MIGR-001, MIGR-002 and MIGR-003]
 |  | TOPAMAX Dosage
Body System/ Adverse Reaction | Placebo (N=45) % | 50 mg/day (N=46) % | 100 mg/day (N=48) %
Body as a Whole – General Disorders
Fatigue | 7 | 7 | 8
Fever | 2 | 4 | 6
Central & Peripheral Nervous System Disorders
Paresthesia | 7 | 20 | 19
Dizziness | 4 | 4 | 6
Gastrointestinal System Disorders
Abdominal pain | 9 | 7 | 15
Nausea | 4 | 4 | 8
Metabolic and Nutritional Disorders
Weight loss | 2 | 7 | 4
Psychiatric Disorders
Anorexia | 4 | 9 | 10
Somnolence | 2 | 2 | 6
Insomnia | 2 | 9 | 2
Resistance Mechanism Disorders
Infection viral | 4 | 4 | 8
Respiratory System Disorders
Upper respiratory tract infection | 11 | 26 | 23
Rhinitis | 2 | 7 | 6
Sinusitis | 2 | 9 | 4
Coughing | 0 | 7 | 2
Special Senses Other, Disorders
Taste perversion | 2 | 2 | 6
Vision Disorders
Conjunctivitis | 4 | 7 | 4

In the double-blind placebo-controlled studies, adverse reactions led to discontinuation of treatment in 8% of placebo patients compared with 6% of TOPAMAX-treated patients. Adverse reactions associated with discontinuing therapy that occurred in more than one TOPAMAX-treated patient were fatigue (1%), headache (1%), and somnolence (1%).

Increased Risk for Bleeding

TOPAMAX is associated with an increased risk for bleeding. In a pooled analysis of placebo-controlled studies of approved and unapproved indications, bleeding was more frequently reported as an adverse reaction for TOPAMAX than for placebo (4.5% versus 3.0% in adult patients, and 4.4% versus 2.3% in pediatric patients). In this analysis, the incidence of serious bleeding events for TOPAMAX and placebo was 0.3% versus 0.2% for adult patients, and 0.4% versus 0% for pediatric patients.

Adverse bleeding reactions reported with TOPAMAX ranged from mild epistaxis, ecchymosis, and increased menstrual bleeding to life-threatening hemorrhages. In patients with serious bleeding events, conditions that increased the risk for bleeding were often present, or patients were often taking drugs that cause thrombocytopenia (other antiepileptic drugs) or affect platelet function or coagulation (e.g., aspirin, nonsteroidal anti-inflammatory drugs, selective serotonin reuptake inhibitors, or warfarin or other anticoagulants).

Other Adverse Reactions Observed During Clinical Trials

Other adverse reactions seen during clinical trials were: abnormal coordination, eosinophilia, gingival bleeding, hematuria, hypotension, myalgia, myopia, postural hypotension, scotoma, suicide attempt, syncope, and visual field defect.

Laboratory Test Abnormalities

Adult Patients

In addition to changes in serum bicarbonate (i.e., metabolic acidosis), sodium chloride and ammonia, TOPAMAX was associated with changes in several clinical laboratory analytes in randomized, double-blind, placebo-controlled studies [see Warnings and Precautions (5.4, 5.12)]. Controlled trials of adjunctive TOPAMAX treatment of adults for partial-onset seizures showed an increased incidence of markedly decreased serum phosphorus (6% TOPAMAX versus 2% placebo), markedly increased serum alkaline phosphatase (3% TOPAMAX versus 1% placebo), and decreased serum potassium (0.4% TOPAMAX versus 0.1% placebo).

Pediatric Patients

In pediatric patients (1–24 months) receiving adjunctive TOPAMAX for partial-onset seizures, there was an increased incidence for an increased result (relative to normal analyte reference range) associated with TOPAMAX (vs placebo) for the following clinical laboratory analytes: creatinine, BUN, alkaline phosphatase, and total protein, The incidence was also increased for a decreased result for bicarbonate (i.e., metabolic acidosis), and potassium with TOPAMAX (vs placebo) [see Use in Specific Populations (8.4)]. TOPAMAX is not indicated for partial-onset seizures in pediatric patients less than 2 years of age.

In pediatric patients (ranging from 6–17 years of age) receiving TOPAMAX for the preventive treatment of migraine, there was an increased incidence for an increased result (relative to normal analyte reference range) associated with TOPAMAX (vs placebo) for the following clinical laboratory analytes: creatinine, BUN, uric acid, chloride, ammonia, alkaline phosphatase, total protein, platelets, and eosinophils, The incidence was also increased for a decreased result for phosphorus, bicarbonate, total white blood count, and neutrophils [see Use in Specific Populations (8.4)] . TOPAMAX is not indicated for the preventive treatment of migraine in pediatric patients less than 12 years of age.

6.2 Postmarketing Experience

The following adverse reactions have been identified during post approval use of TOPAMAX. Because these reactions are reported voluntarily from a population of uncertain size, it is not always possible to reliably estimate their frequency or establish a causal relationship to drug exposure.

Body as a Whole-General Disorders:oligohydrosis and hyperthermia [see Warnings and Precautions (5.3)] , hyperammonemia, hyperammonemic encephalopathy [see Warnings and Precautions (5.12)], hypothermia with concomitant valproic acid [see Warnings and Precautions (5.14)]

Gastrointestinal System Disorders:hepatic failure (including fatalities), hepatitis, pancreatitis

Skin and Appendage Disorders:bullous skin reactions (including erythema multiforme, Stevens-Johnson syndrome, toxic epidermal necrolysis) [see Warnings and Precautions (5.11)] , pemphigus

Urinary System Disorders:kidney stones, nephrocalcinosis [see Warnings and Precautions (5.4, 5.13)]

Vision Disorders:acute myopia, secondary angle closure glaucoma [see Warnings and Precautions (5.1)] , maculopathy

Hematological Disorders:decrease of the International Normalized Ratio (INR) or prothrombin time when given concomitantly with vitamin K antagonist anticoagulant medications such as warfarin.

7 DRUG INTERACTIONS

7.1 Antiepileptic Drugs

Concomitant administration of phenytoin or carbamazepine with TOPAMAX resulted in a clinically significant decrease in plasma concentrations of topiramate when compared to TOPAMAX given alone. A dosage adjustment may be needed [see Dosage and Administration (2.1), Clinical Pharmacology (12.3)].

Concomitant administration of valproic acid and TOPAMAX has been associated with hypothermia and hyperammonemia with and without encephalopathy. Examine blood ammonia levels in patients in whom the onset of hypothermia has been reported [see Warnings and Precautions (5.12, 5.14), Clinical Pharmacology (12.3)] .

7.2 Other Carbonic Anhydrase Inhibitors

Concomitant use of topiramate, a carbonic anhydrase inhibitor, with any other carbonic anhydrase inhibitor (e.g., zonisamide or acetazolamide) may increase the severity of metabolic acidosis and may also increase the risk of kidney stone formation. Therefore, patients given TOPAMAX concomitantly with another carbonic anhydrase inhibitor should be monitored particularly closely for the appearance or worsening of metabolic acidosis [see Clinical Pharmacology (12.3)] .

7.3 CNS Depressants

Concomitant administration of TOPAMAX and alcohol or other CNS depressant drugs has not been evaluated in clinical studies. Because of the potential of topiramate to cause CNS depression, as well as other cognitive and/or neuropsychiatric adverse reactions, TOPAMAX should be used with extreme caution if used in combination with alcohol and other CNS depressants.

7.4 Contraceptives

The possibility of decreased contraceptive efficacy and increased breakthrough bleeding may occur in patients taking contraceptive products with TOPAMAX. Patients taking estrogen-containing or progestin-only contraceptives should be asked to report any change in their bleeding patterns. Contraceptive efficacy can be decreased even in the absence of breakthrough bleeding [see Clinical Pharmacology (12.3)].

7.5 Hydrochlorothiazide (HCTZ)

Topiramate Cmaxand AUC increased when HCTZ was added to TOPAMAX. The clinical significance of this change is unknown. The addition of HCTZ to TOPAMAX may require a decrease in the TOPAMAX dose [see Clinical Pharmacology (12.3)] .

7.6 Pioglitazone

A decrease in the exposure of pioglitazone and its active metabolites were noted with the concurrent use of pioglitazone and TOPAMAX in a clinical trial. The clinical relevance of these observations is unknown; however, when TOPAMAX is added to pioglitazone therapy or pioglitazone is added to TOPAMAX therapy, careful attention should be given to the routine monitoring of patients for adequate control of their diabetic disease state [see Clinical Pharmacology (12.3)] .

7.7 Lithium

An increase in systemic exposure of lithium following TOPAMAX doses of up to 600 mg/day can occur. Lithium levels should be monitored when co-administered with high-dose TOPAMAX [see Clinical Pharmacology (12.3)] .

7.8 Amitriptyline

Some patients may experience a large increase in amitriptyline concentration in the presence of TOPAMAX and any adjustments in amitriptyline dose should be made according to the patient's clinical response and not on the basis of plasma levels [see Clinical Pharmacology (12.3)] .

8 USE IN SPECIFIC POPULATIONS

8.1 Pregnancy

Pregnancy Exposure Registry

There is a pregnancy exposure registry that monitors pregnancy outcomes in women exposed to TOPAMAX during pregnancy. Patients should be encouraged to enroll in the North American Antiepileptic Drug (NAAED) Pregnancy Registry if they become pregnant. This registry is collecting information about the safety of antiepileptic drugs during pregnancy. To enroll, patients can call the toll-free number 1-888-233-2334. Information about the North American Drug Pregnancy Registry can be found at http://www.aedpregnancyregistry.org/ .

Risk Summary

TOPAMAX can cause fetal harm when administered to a pregnant woman. Data from pregnancy registries indicate that infants exposed to topiramate in uterohave an increased risk of major congenital malformations, including but not limited to cleft lip and/or cleft palate (oral clefts), and of being small for gestational age (SGA) [see Human Data] . SGA has been observed at all doses and appears to be dose-dependent. The prevalence of SGA is greater in infants of women who received higher doses of topiramate during pregnancy. In addition, the prevalence of SGA in infants of women who continued topiramate use until later in pregnancy is higher compared to the prevalence in infants of women who stopped topiramate use before the third trimester.

In multiple animal species, topiramate produced developmental toxicity, including increased incidences of fetal malformations, in the absence of maternal toxicity at clinically relevant doses [see Animal Data] .

All pregnancies have a background risk of birth defects, loss, or other adverse outcomes. The estimated background risk of major birth defects and miscarriage for the indicated population is unknown. In the U.S. general population, the estimated background risks of major birth defects and miscarriage in clinically recognized pregnancies are 2–4% and 15–20%, respectively.

Clinical Considerations

Fetal/Neonatal Adverse Reactions

Consider the benefits and risks of topiramate when prescribing this drug to women of childbearing potential, particularly when topiramate is considered for a condition not usually associated with permanent injury or death. Because of the risk of oral clefts to the fetus, which occur in the first trimester of pregnancy, all women of childbearing potential should be informed of the potential risk to the fetus from exposure to topiramate. Women who are planning a pregnancy should be counseled regarding the relative risks and benefits of topiramate use during pregnancy, and alternative therapeutic options should be considered for these patients.

Labor or Delivery

Although the effect of TOPAMAX on labor and delivery in humans has not been established, the development of topiramate-induced metabolic acidosis in the mother and/or in the fetus might affect the fetus' ability to tolerate labor.

TOPAMAX treatment can cause metabolic acidosis [see Warnings and Precautions (5.4)]. The effect of topiramate-induced metabolic acidosis has not been studied in pregnancy; however, metabolic acidosis in pregnancy (due to other causes) can cause decreased fetal growth, decreased fetal oxygenation, and fetal death, and may affect the fetus' ability to tolerate labor. Pregnant patients should be monitored for metabolic acidosis and treated as in the nonpregnant state [see Warnings and Precautions (5.4)]. Newborns of mothers treated with TOPAMAX should be monitored for metabolic acidosis because of transfer of topiramate to the fetus and possible occurrence of transient metabolic acidosis following birth.

Based on limited information, topiramate has also been associated with pre-term labor and premature delivery.

Data

Human Data

Data from pregnancy registries indicate an increased risk of major congenital malformations, including but not limited to oral clefts in infants exposed to topiramate during the first trimester of pregnancy. Other than oral clefts, no specific pattern of major congenital malformations or grouping of major congenital malformation types were observed. In the NAAED pregnancy registry, when topiramate-exposed infants with only oral clefts were excluded, the prevalence of major congenital malformations (4.1%) was higher than that in infants exposed to a reference AED (1.8%) or in infants with mothers without epilepsy and without exposure to AEDs (1.1%). The prevalence of oral clefts among topiramate-exposed infants (1.4%) was higher than the prevalence in infants exposed to a reference AED (0.3%) or the prevalence in infants with mothers without epilepsy and without exposure to AEDs (0.11%). It was also higher than the background prevalence in United States (0.17%) as estimated by the Centers for Disease Control and Prevention (CDC). The relative risk of oral clefts in topiramate-exposed pregnancies in the NAAED Pregnancy Registry was 12.5 (95% Confidence Interval [CI] 5.9–26.37) as compared to the risk in a background population of untreated women. The UK Epilepsy and Pregnancy Register reported a prevalence of oral clefts among infants exposed to topiramate monotherapy (3.2%) that was 16 times higher than the background rate in the UK (0.2%).

Data from the NAAED pregnancy registry and a population-based birth registry cohort indicate that exposure to topiramate in uterois associated with an increased risk of SGA newborns (birth weight <10th percentile). In the NAAED pregnancy registry, 19.7% of topiramate-exposed newborns were SGA compared to 7.9% of newborns exposed to a reference AED and 5.4% of newborns of mothers without epilepsy and without AED exposure. In the Medical Birth Registry of Norway (MBRN), a population-based pregnancy registry, 25% of newborns in the topiramate monotherapy exposure group were SGA compared to 9% in the comparison group unexposed to AEDs. The long-term consequences of the SGA findings are not known.

Animal Data

When topiramate (0, 20, 100, or 500 mg/kg/day) was administered to pregnant mice during the period of organogenesis, incidences of fetal malformations (primarily craniofacial defects) were increased at all doses. Fetal body weights and skeletal ossification were reduced at the highest dose tested in conjunction with decreased maternal body weight gain. A no-effect dose for embryofetal developmental toxicity in mice was not identified. The lowest dose tested, which was associated with increased malformations, is less than the maximum recommended human dose (MRHD) for epilepsy (400 mg/day) or migraine (100 mg/day) on a body surface area (mg/m^2) basis.

In pregnant rats administered topiramate (0, 20, 100, and 500 mg/kg/day or 0, 0.2, 2.5, 30, and 400 mg/kg/day) orally during the period of organogenesis, the frequency of limb malformations (ectrodactyly, micromelia, and amelia) was increased in fetuses at 400 and 500 mg/kg/day. Embryotoxicity (reduced fetal body weights, increased incidences of structural variations) was observed at doses as low as 20 mg/kg/day. Clinical signs of maternal toxicity were seen at 400 mg/kg/day and above, and maternal body weight gain was reduced at doses of 100 mg/kg/day or greater. The no-effect dose (2.5 mg/kg/day) for embryofetal developmental toxicity in rats is less than the MRHD for epilepsy or migraine on a mg/m^2basis.

In pregnant rabbits administered topiramate (0, 20, 60, and 180 mg/kg/day or 0, 10, 35, and 120 mg/kg/day) orally during organogenesis, embryofetal mortality was increased at 35 mg/kg/day, and increased incidences of fetal malformations (primarily rib and vertebral malformations) were observed at 120 mg/kg/day. Evidence of maternal toxicity (decreased body weight gain, clinical signs, and/or mortality) was seen at 35 mg/kg/day and above. The no-effect dose (20 mg/kg/day) for embryofetal developmental toxicity in rabbits is equivalent to the MRHD for epilepsy and approximately 4 times the MRHD for migraine on a mg/m^2basis.

When topiramate (0, 0.2, 4, 20, and 100 mg/kg/day or 0, 2, 20, and 200 mg/kg/day) was administered orally to female rats during the latter part of gestation and throughout lactation, offspring exhibited decreased viability and delayed physical development at 200 mg/kg/day and reductions in pre- and/or postweaning body weight gain at 2 mg/kg/day and above. Maternal toxicity (decreased body weight gain, clinical signs) was evident at 100 mg/kg/day or greater. In a rat embryofetal development study which included postnatal assessment of offspring, oral administration of topiramate (0, 0.2, 2.5, 30, and 400 mg/kg) to pregnant animals during the period of organogenesis resulted in delayed physical development in offspring at 400 mg/kg/day and persistent reductions in body weight gain in offspring at 30 mg/kg/day and higher. The no-effect dose (0.2 mg/kg/day) for pre- and postnatal developmental toxicity in rats is less than the MRHD for epilepsy or migraine on a mg/m^2basis.

8.2 Lactation

Risk Summary

Topiramate is excreted in human milk [see Data] . The effects of topiramate on milk production are unknown. Diarrhea and somnolence have been reported in breastfed infants whose mothers receive topiramate treatment.

The developmental and health benefits of breastfeeding should be considered along with the mother's clinical need for TOPAMAX and any potential adverse effects on the breastfed infant from TOPAMAX or from the underlying maternal condition.

Data

Human Data

Limited data from 5 women with epilepsy treated with topiramate during lactation showed drug levels in milk similar to those in maternal plasma.

8.3 Females and Males of Reproductive Potential

Contraception

Women of childbearing potential who are not planning a pregnancy should use effective contraception because of the risk of major congenital malformations, including oral clefts, and the risk of infants being SGA [see Drug Interactions (7.4)and Use in Specific Populations (8.1)] .

8.4 Pediatric Use

Adjunctive Treatment for Epilepsy

Pediatric Patients 2 Years of Age and Older

The safety and effectiveness of TOPAMAX as adjunctive therapy for the treatment of partial-onset seizures, primary generalized tonic-clonic seizures, or seizures associated with Lennox-Gastaut syndrome have been established in pediatric patients 2 years of age and older [see Adverse Reactions (6.1)and Clinical Studies (14.2)] .

Pediatric Patients Below the Age of 2 Years

Safety and effectiveness in patients below the age of 2 years have not been established for the adjunctive therapy treatment of partial-onset seizures, primary generalized tonic-clonic seizures, or seizures associated with Lennox-Gastaut syndrome. In a single randomized, double-blind, placebo-controlled investigational trial, the efficacy, safety, and tolerability of topiramate oral liquid and sprinkle formulations as an adjunct to concurrent antiepileptic drug therapy in pediatric patients 1 to 24 months of age with refractory partial-onset seizures were assessed. After 20 days of double-blind treatment, topiramate (at fixed doses of 5, 15, and 25 mg/kg/day) did not demonstrate efficacy compared with placebo in controlling seizures.

In general, the adverse reaction profile for TOPAMAX in this population was similar to that of older pediatric patients, although results from the above controlled study and an open-label, long-term extension study in these pediatric patients 1 to 24 months old suggested some adverse reactions/toxicities (not previously observed in older pediatric patients and adults; i.e., growth/length retardation, certain clinical laboratory abnormalities, and other adverse reactions/toxicities that occurred with a greater frequency and/or greater severity than had been recognized previously from studies in older pediatric patients or adults for various indications).

These very young pediatric patients appeared to experience an increased risk for infections (any topiramate dose 12%, placebo 0%) and of respiratory disorders (any topiramate dose 40%, placebo 16%). The following adverse reactions were observed in at least 3% of patients on topiramate and were 3% to 7% more frequent than in patients on placebo: viral infection, bronchitis, pharyngitis, rhinitis, otitis media, upper respiratory infection, cough, and bronchospasm. A generally similar profile was observed in older pediatric patients [see Adverse Reactions (6)] .

Topiramate resulted in an increased incidence of patients with increased creatinine (any topiramate dose 5%, placebo 0%), BUN (any topiramate dose 3%, placebo 0%), and protein (any topiramate dose 34%, placebo 6%), and an increased incidence of decreased potassium (any topiramate dose 7%, placebo 0%). This increased frequency of abnormal values was not dose-related. Creatinine was the only analyte showing a noteworthy increased incidence (topiramate 25 mg/kg/day 5%, placebo 0%) of a markedly abnormal increase. The significance of these findings is uncertain.

Topiramate treatment also produced a dose-related increase in the percentage of patients who had a shift from normal at baseline to high/increased (above the normal reference range) in total eosinophil count at the end of treatment. The incidence of these abnormal shifts was 6% for placebo, 10% for 5 mg/kg/day, 9% for 15 mg/kg/day, 14% for 25 mg/kg/day, and 11% for any topiramate dose. There was a mean dose-related increase in alkaline phosphatase. The significance of these findings is uncertain.

Topiramate produced a dose-related increased incidence of hyperammonemia [see Warnings and Precautions (5.12)] .

Treatment with topiramate for up to 1 year was associated with reductions in Z SCORES for length, weight, and head circumference [see Warnings and Precautions (5.4), Adverse Reactions (6)] .

In open-label, uncontrolled experience, increasing impairment of adaptive behavior was documented in behavioral testing over time in this population. There was a suggestion that this effect was dose-related. However, because of the absence of an appropriate control group, it is not known if this decrement in function was treatment-related or reflects the patient's underlying disease (e.g., patients who received higher doses may have more severe underlying disease) [see Warnings and Precautions (5.6)] .

In this open-label, uncontrolled study, the mortality was 37 deaths/1000 patient years. It is not possible to know whether this mortality rate is related to topiramate treatment, because the background mortality rate for a similar, significantly refractory, young pediatric population (1–24 months) with partial epilepsy is not known.

Monotherapy Treatment for Epilepsy

Pediatric Patients 2 Years of Age and Older

The safety and effectiveness of TOPAMAX as monotherapy for the treatment of partial-onset seizures or primary generalized tonic-clonic seizures have been established in pediatric patients aged 2 years and older [see Adverse Reactions (6.1), Clinical Studies (14.1)] .

A one-year, active-controlled, open-label study with blinded assessments of bone mineral density (BMD) and growth in pediatric patients 4 to 15 years of age, including 63 patients with recent or new onset of epilepsy, was conducted to assess effects of TOPAMAX (N=28, 6–15 years of age) versus levetiracetam (N=35, 4–15 years of age) monotherapy on bone mineralization and on height and weight, which reflect growth. Effects on bone mineralization were evaluated via dual-energy X-ray absorptiometry and blood markers. Table 10 summarizes effects of TOPAMAX at 12 months for key safety outcomes including BMD, height, height velocity, and weight. All Least Square Mean values for TOPAMAX and the comparator were positive. Therefore, the Least Square Mean treatment differences shown reflect a TOPAMAX-induced attenuation of the key safety outcomes. Statistically significant effects were observed for decreases in BMD (and bone mineral content) in lumbar spine and total body less head and in weight. Subgroup analyses according to age demonstrated similar negative effects for all key safety outcomes (i.e., BMD, height, weight).

Table 10: Summary of TOPAMAX Treatment Difference Results at 12 Months for Key Safety Outcomes
Safety Parameter | Treatment Difference in Least Square Means (95 % Confidence Interval)
Annual Change in BMD Lumbar Spine (g/cm^2) | -0.036 (-0.058, -0.014)
Annual Change in BMD TBLH [TBLH=total body less head] (g/cm^2) | -0.026 (-0.039, -0.012)
Annual Change in Height (cm) (4–9 years, Primary Analysis Population for Height) [Whereas no patients were randomized to 2–5 year age subgroup for TOPAMAX, 5 patients (4–5 years) were randomized to the active control group.] | -0.84 (-2.67, 0.99)
Annual Change in Height (cm) (4–15 years) | -0.75 (-2.21, 0.71)
Annual Change in Height (cm) (10–15 years) | -1.01 (-3.64, 1.61)
Height Velocity (cm/year) (4–9 years) | -1.00 (-2.76, 0.76)
Height Velocity (cm/year) (4–15 years) | -0.98 (-2.33, 0.37)
Height Velocity (cm/year) (10–15 years) | -0.96 (-3.24, 1.32)
Annual Change in Weight (kg) | -2.05 (-3.66, -0.45)

Metabolic acidosis (serum bicarbonate < 20 mEq/L) was observed in all TOPAMAX-treated patients at some time in the study [see Warnings and Precautions (5.4)] . Over the whole study, 76% more TOPAMAX-treated patients experienced persistent metabolic acidosis (i.e. 2 consecutive visits with or final serum bicarbonate < 20 mEq/L) compared to levetiracetam -treated patients. Over the whole study, 35% more TOPAMAX-treated patients experienced a markedly abnormally low serum bicarbonate (i.e., absolute value < 17 mEq/L and ≥ 5 mEq/L decrease from pre-treatment), indicating the frequency of more severe metabolic acidosis, compared to levetiracetam -treated patients. The decrease in BMD at 12 months was correlated with decreased serum bicarbonate, suggesting that metabolic acidosis was at least a partial factor contributing to this adverse effect on BMD.

TOPAMAX-treated patients exhibited an increased risk for developing an increased serum creatinine and an increased serum glucose above the normal reference range compared to control patients.

Pediatric Patients Below the Age of 2 Years

Safety and effectiveness in patients below the age of 2 years have not been established for the monotherapy treatment of epilepsy.

Preventive Treatment of Migraine

Pediatric Patients 12 to 17 Years of Age

Safety and effectiveness of topiramate for the preventive treatment of migraine was studied in 5 double-blind, randomized, placebo-controlled, parallel-group trials in a total of 219 pediatric patients, at doses of 50 to 200 mg/day, or 2 to 3 mg/kg/day. These comprised a fixed dose study in 103 pediatric patients 12 to 17 years of age [see Clinical Studies (14.3)] , a flexible dose (2 to 3 mg/kg/day), placebo-controlled study in 157 pediatric patients 6 to 16 years of age (including 67 pediatric patients 12 to 16 years of age), and a total of 49 pediatric patients 12 to 17 years of age in 3 studies for the preventive treatment of migraine primarily in adults. Open-label extension phases of 3 studies enabled evaluation of long-term safety for up to 6 months after the end of the double-blind phase.

Efficacy of topiramate for the preventive treatment of migraine in pediatric patients 12 to 17 years of age is demonstrated for a 100 mg daily dose in Study 13 [see Clinical Studies (14.3)]. Efficacy of topiramate (2 to 3 mg/kg/day) for the preventive treatment of migraine was not demonstrated in a placebo-controlled trial of 157 pediatric patients (6 to 16 years of age) that included treatment of 67 pediatric patients (12 to 16 years of age) for 20 weeks.

In the pediatric trials (12 to 17 years of age) in which patients were randomized to placebo or a fixed daily dose of TOPAMAX, the most common adverse reactions with TOPAMAX that were seen at an incidence higher (≥5%) than in the placebo group were: paresthesia, upper respiratory tract infection, anorexia, and abdominal pain [see Adverse Reactions (6)] .

The most common cognitive adverse reaction in pooled double-blind studies in pediatric patients 12 to 17 years of age was difficulty with concentration/attention [see Warnings and Precautions (5.6)].

Markedly abnormally low serum bicarbonate values indicative of metabolic acidosis were reported in topiramate-treated pediatric migraine patients [see Warnings and Precautions (5.4)] .

In topiramate-treated pediatric patients (12 to 17 years of age) compared to placebo-treated patients, abnormally increased results were more frequent for creatinine, BUN, uric acid, chloride, ammonia, total protein, and platelets. Abnormally decreased results were observed with topiramate vs placebo treatment for phosphorus and bicarbonate [see Adverse Reactions (6.1)] .

Notable changes (increases and decreases) from baseline in systolic blood pressure, diastolic blood pressure, and pulse were observed occurred more commonly in pediatric patients treated with topiramate compared to pediatric patients treated with placebo [see Clinical Pharmacology (12.2)].

Pediatric Patients Below the Age of 12 Years

Safety and effectiveness in pediatric patients below the age of 12 years have not been established for the preventive treatment of migraine.

In a double-blind study in 90 pediatric patients 6 to 11 years of age (including 59 topiramate-treated and 31 placebo patients), the adverse reaction profile was generally similar to that seen in pooled double-blind studies of pediatric patients 12 to 17 years of age. The most common adverse reactions that occurred in TOPAMAX-treated pediatric patients 6 to 11 years of age, and at least twice as frequently than placebo, were gastroenteritis (12% topiramate, 6% placebo), sinusitis (10% topiramate, 3% placebo), weight loss (8% topiramate, 3% placebo) and paresthesia (7% topiramate, 0% placebo). Difficulty with concentration/attention occurred in 3 topiramate-treated patients (5%) and 0 placebo-treated patients.

The risk for cognitive adverse reaction was greater in younger patients (6 to 11 years of age) than in older patients (12 to 17 years of age) [see Warnings and Precautions (5.6)] .

Juvenile Animal Studies

When topiramate (0, 30, 90, and 300 mg/kg/day) was administered orally to rats during the juvenile period of development (postnatal days 12 to 50), bone growth plate thickness was reduced in males at the highest dose. The no-effect dose (90 mg/kg/day) for adverse developmental effects is approximately 2 times the maximum recommended pediatric dose (9 mg/kg/day) on a body surface area (mg/m^2) basis.

8.5 Geriatric Use

In clinical trials, 3% of patients were over age 60. No age-related differences in effectiveness or adverse effects were evident. However, clinical studies of topiramate did not include sufficient numbers of subjects age 65 and over to determine whether they respond differently than younger subjects. Dosage adjustment may be necessary for elderly with age-related renal impairment (creatinine clearance rate <70 mL/min/1.73 m^2) resulting in reduced clearance [see Dosage and Administration (2.5), Clinical Pharmacology (12.3)] .

8.6 Renal Impairment

The clearance of topiramate is reduced in patients with moderate (creatinine clearance 30 to 69 mL/min/1.73 m^2) and severe (creatinine clearance <30 mL/min/1.73 m^2) renal impairment. A dosage adjustment is recommended in patients with moderate or severe renal impairment [see Dosage and Administration (2.5), Clinical Pharmacology (12.3)] .

8.7 Patients Undergoing Hemodialysis

Topiramate is cleared by hemodialysis at a rate that is 4 to 6 times greater than in a normal individual. A dosage adjustment may be required [see Dosage and Administration (2.6), Clinical Pharmacology (12.3)].

10 OVERDOSAGE

Overdoses of TOPAMAX have been reported. Signs and symptoms included convulsions, drowsiness, speech disturbance, blurred vision, diplopia, impaired mentation, lethargy, abnormal coordination, stupor, hypotension, abdominal pain, agitation, dizziness and depression. The clinical consequences were not severe in most cases, but deaths have been reported after overdoses involving TOPAMAX.

TOPAMAX overdose has resulted in severe metabolic acidosis [see Warnings and Precautions (5.4)] .

A patient who ingested a dose of TOPAMAX between 96 and 110 g was admitted to a hospital with a coma lasting 20 to 24 hours followed by full recovery after 3 to 4 days.

In the event of overdose, TOPAMAX should be discontinued and general supportive treatment given until clinical toxicity has been diminished or resolved. Hemodialysis is an effective means of removing topiramate from the body.

11 DESCRIPTION

Topiramate is a sulfamate-substituted monosaccharide. TOPAMAX®(topiramate) Tablets are available as 25 mg, 50 mg, 100 mg, and 200 mg round tablets for oral administration. TOPAMAX (topiramate capsules) Sprinkle Capsules are available as 15 mg and 25 mg sprinkle capsules for oral administration as whole capsules or opened and sprinkled onto soft food.

Topiramate is a white crystalline powder with a bitter taste. Topiramate is most soluble in alkaline solutions containing sodium hydroxide or sodium phosphate and having a pH of 9 to 10. It is freely soluble in acetone, chloroform, dimethylsulfoxide, and ethanol. The solubility in water is 9.8 mg/mL. Its saturated solution has a pH of 6.3. Topiramate has the molecular formula C12H21NO8S and a molecular weight of 339.36. Topiramate is designated chemically as 2,3:4,5-Di- O-isopropylidene-β-D-fructopyranose sulfamate and has the following structural formula:

TOPAMAX Tablets contain the following inactive ingredients: carnauba wax, hypromellose, lactose monohydrate, magnesium stearate, microcrystalline cellulose, polyethylene glycol, polysorbate 80, pregelatinized starch, purified water, sodium starch glycolate, synthetic iron oxide, and titanium dioxide.

TOPAMAX Sprinkle Capsules contain topiramate-coated beads in a hard gelatin capsule. The inactive ingredients are black pharmaceutical ink, cellulose acetate, gelatin, povidone, sodium lauryl sulfate, sorbitan monolaurate, sugar spheres (sucrose and starch) and titanium dioxide.

12 CLINICAL PHARMACOLOGY

12.1 Mechanism of Action

The precise mechanisms by which topiramate exerts its anticonvulsant and preventive migraine effects are unknown; however, preclinical studies have revealed four properties that may contribute to topiramate's efficacy for epilepsy and the preventive treatment of migraine. Electrophysiological and biochemical evidence suggests that topiramate, at pharmacologically relevant concentrations, blocks voltage-dependent sodium channels, augments the activity of the neurotransmitter gamma-aminobutyrate at some subtypes of the GABA-A receptor, antagonizes the AMPA/kainate subtype of the glutamate receptor, and inhibits the carbonic anhydrase enzyme, particularly isozymes II and IV.

12.2 Pharmacodynamics

Topiramate has anticonvulsant activity in rat and mouse maximal electroshock seizure (MES) tests. Topiramate is only weakly effective in blocking clonic seizures induced by the GABAAreceptor antagonist, pentylenetetrazole. Topiramate is also effective in rodent models of epilepsy, which include tonic and absence-like seizures in the spontaneous epileptic rat (SER) and tonic and clonic seizures induced in rats by kindling of the amygdala or by global ischemia.

Changes (increases and decreases) from baseline in vital signs (systolic blood pressure-SBP, diastolic blood pressure-DBP, pulse) occurred more frequently in pediatric patients (6 to 17 years) treated with various daily doses of topiramate (50 mg, 100 mg, 200 mg, 2 to 3 mg/kg) than in patients treated with placebo in controlled trials for the preventive treatment of migraine. The most notable changes were SBP <90 mm Hg, DBP <50 mm Hg, SBP or DBP increases or decreases ≥20 mm Hg, and pulse increases or decreases ≥30 beats per minute. These changes were often dose-related, and were most frequently associated with the greatest treatment difference at the 200 mg dose level. Systematic collection of orthostatic vital signs has not been conducted. The clinical significance of these various changes in vital signs has not been clearly established.

12.3 Pharmacokinetics

The sprinkle formulation is bioequivalent to the immediate-release tablet formulation and, therefore, may be substituted as a therapeutic equivalent.

Absorption of topiramate is rapid, with peak plasma concentrations occurring at approximately 2 hours following a 400 mg oral dose. The relative bioavailability of topiramate from the tablet formulation is about 80% compared to a solution. The bioavailability of topiramate is not affected by food.

The pharmacokinetics of topiramate are linear with dose proportional increases in plasma concentration over the dose range studied (200 to 800 mg/day). The mean plasma elimination half-life is 21 hours after single or multiple doses. Steady-state is thus reached in about 4 days in patients with normal renal function. Topiramate is 15% to 41% bound to human plasma proteins over the blood concentration range of 0.5 to 250 µg/mL. The fraction bound decreased as blood concentration increased.

Carbamazepine and phenytoin do not alter the binding of topiramate. Sodium valproate, at 500 µg/mL (a concentration 5 to 10 times higher than considered therapeutic for valproate) decreased the protein binding of topiramate from 23% to 13%. Topiramate does not influence the binding of sodium valproate.

Metabolism and Excretion

Topiramate is not extensively metabolized and is primarily eliminated unchanged in the urine (approximately 70% of an administered dose). Six metabolites have been identified in humans, none of which constitutes more than 5% of an administered dose. The metabolites are formed via hydroxylation, hydrolysis, and glucuronidation. There is evidence of renal tubular reabsorption of topiramate. In rats, given probenecid to inhibit tubular reabsorption, along with topiramate, a significant increase in renal clearance of topiramate was observed. This interaction has not been evaluated in humans. Overall, oral plasma clearance (CL/F) is approximately 20 to 30 mL/min in adults following oral administration.

Specific Populations

Renal Impairment

The clearance of topiramate was reduced by 42% in subjects with moderate renal impairment (creatinine clearance 30 to 69 mL/min/1.73 m^2) and by 54% in subjects with severe renal impairment (creatinine clearance <30 mL/min/1.73 m^2) compared to subjects with normal renal function (creatinine clearance >70 mL/min/1.73 m^2) [see Dosage and Administration (2.4)and (2.5)] .

Hemodialysis

Topiramate is cleared by hemodialysis. Using a high-efficiency, counterflow, single pass-dialysate hemodialysis procedure, topiramate dialysis clearance was 120 mL/min with blood flow through the dialyzer at 400 mL/min. This high clearance (compared to 20 to 30 mL/min total oral clearance in healthy adults) will remove a clinically significant amount of topiramate from the patient over the hemodialysis treatment period [see Dosage and Administration (2.6), Use in Specific Populations (8.7)] .

Hepatic Impairment

Plasma clearance of topiramate decreased a mean of 26% in patients with moderate to severe hepatic impairment.

Age, Gender, and Race

The pharmacokinetics of topiramate in elderly subjects (65 to 85 years of age, N=16) were evaluated in a controlled clinical study. The elderly subject population had reduced renal function (creatinine clearance [-20%]) compared to young adults. Following a single oral 100 mg dose, maximum plasma concentration for elderly and young adults was achieved at approximately 1 to 2 hours. Reflecting the primary renal elimination of topiramate, topiramate plasma and renal clearance were reduced 21% and 19%, respectively, in elderly subjects, compared to young adults. Similarly, topiramate half-life was longer (13%) in the elderly. Reduced topiramate clearance resulted in slightly higher maximum plasma concentration (23%) and AUC (25%) in elderly subjects than observed in young adults. Topiramate clearance is decreased in the elderly only to the extent that renal function is reduced [see Dosage and Administration (2.4)and Use in Specific Populations (8.5)] .

Clearance of topiramate in adults was not affected by gender or race.

Pediatric Pharmacokinetics

Pharmacokinetics of topiramate were evaluated in patients age 2 to <16 years. Patients received either no or a combination of other antiepileptic drugs. A population pharmacokinetic model was developed on the basis of pharmacokinetic data from relevant topiramate clinical studies. This dataset contained data from 1217 subjects including 258 pediatric patients age 2 to <16 years (95 pediatric patients <10 years of age).

Pediatric patients on adjunctive treatment exhibited a higher oral clearance (L/h) of topiramate compared to patients on monotherapy, presumably because of increased clearance from concomitant enzyme-inducing antiepileptic drugs. In comparison, topiramate clearance per kg is greater in pediatric patients than in adults and in young pediatric patients (down to 2 years) than in older pediatric patients. Consequently, the plasma drug concentration for the same mg/kg/day dose would be lower in pediatric patients compared to adults and also in younger pediatric patients compared to older pediatric patients. Clearance was independent of dose.

As in adults, hepatic enzyme-inducing antiepileptic drugs decrease the steady state plasma concentrations of topiramate.

Pediatric Patients with Obesity

A population PK analysis of topiramate was conducted in 129 children <21 years of age with and without obesity to evaluate the potential impact of obesity on plasma topiramate exposures. Obesity was defined as BMI ≥ 95th percentile for age and sex based on CDC-recommended BMI-for-age growth charts for males and females. Using the currently recommended dosing regimens, children with obesity are likely to have median values of average concentration at steady-state and trough concentration at steady-state up to 20% lower and 19% lower, respectively, compared to children without obesity. Dosage adjustment according to obesity status is not necessary.

Drug Interactions

In vitrostudies indicate that topiramate does not inhibit CYP1A2, CYP2A6, CYP2B6, CYP2C9, CYP2D6, CYP2E1, or CYP3A4/5 isozymes. In vitrostudies indicate that topiramate is a mild inhibitor of CYP2C19 and a mild inducer of CYP3A4.

Antiepileptic Drugs

Potential interactions between topiramate and standard AEDs were assessed in controlled clinical pharmacokinetic studies in patients with epilepsy. The effects of these interactions on mean plasma AUCs are summarized in Table 11.

In Table 11, the second column (AED concentration) describes what happens to the concentration of the co-administered AED listed in the first column when topiramate is added. The third column (topiramate concentration) describes how the co-administration of a drug listed in the first column modifies the concentration of topiramate when compared to TOPAMAX given alone.

Table 11: Summary of AED Interactions with TOPAMAX
AED Co-administered | AED Concentration | Topiramate Concentration
Phenytoin | NC or 25% increase [Plasma concentration increased 25% in some patients, generally those on a twice a day dosing regimen of phenytoin.] | 48% decrease
Carbamazepine (CBZ) | NC | 40% decrease
CBZ epoxide [Is not administered but is an active metabolite of carbamazepine.] | NC | NE
Valproic acid | 11% decrease | 14% decrease
Phenobarbital | NC | NE
Primidone | NC | NE
Lamotrigine | NC at TPM doses up to 400 mg/day | 13% decrease
NC = Less than 10% change in plasma concentration.
AED = Antiepileptic drug.
NE = Not Evaluated.
TPM = Topiramate

Oral Contraceptives

In a pharmacokinetic interaction study in healthy volunteers with a concomitantly administered combination oral contraceptive product containing 1 mg norethindrone (NET) plus 35 mcg ethinyl estradiol (EE), TOPAMAX, given in the absence of other medications at doses of 50 to 200 mg/day, was not associated with statistically significant changes in mean exposure (AUC) to either component of the oral contraceptive. In another study, exposure to EE was statistically significantly decreased at doses of 200, 400, and 800 mg/day (18%, 21%, and 30%, respectively) when given as adjunctive therapy in patients taking valproic acid. In both studies, TOPAMAX (50 mg/day to 800 mg/day) did not significantly affect exposure to NET and there was no significant dose-dependent change in EE exposure for doses of 50 to 200 mg/day. The clinical significance of the changes observed is not known [see Drug Interactions (7.4)] .

Digoxin

In a single-dose study, serum digoxin AUC was decreased by 12% with concomitant TOPAMAX administration. The clinical relevance of this observation has not been established.

Hydrochlorothiazide

A drug interaction study conducted in healthy volunteers evaluated the steady-state pharmacokinetics of hydrochlorothiazide (HCTZ) (25 mg every 24 hours) and topiramate (96 mg every 12 hours) when administered alone and concomitantly. The results of this study indicate that topiramate Cmaxincreased by 27% and AUC increased by 29% when HCTZ was added to topiramate. The clinical significance of this change is unknown. The steady-state pharmacokinetics of HCTZ were not significantly influenced by the concomitant administration of topiramate. Clinical laboratory results indicated decreases in serum potassium after topiramate or HCTZ administration, which were greater when HCTZ and topiramate were administered in combination.

Metformin

A drug interaction study conducted in healthy volunteers evaluated the steady-state pharmacokinetics of metformin (500 mg every 12 hours) and topiramate in plasma when metformin was given alone and when metformin and topiramate (100 mg every 12 hours) were given simultaneously. The results of this study indicated that the mean metformin Cmaxand AUC0–12hincreased by 18% and 25%, respectively, when topiramate was added. Topiramate did not affect metformin tmax. The clinical significance of the effect of topiramate on metformin pharmacokinetics is not known. Oral plasma clearance of topiramate appears to be reduced when administered with metformin. The clinical significance of the effect of metformin on topiramate pharmacokinetics is unclear.

Pioglitazone

A drug interaction study conducted in healthy volunteers evaluated the steady-state pharmacokinetics of topiramate and pioglitazone when administered alone and concomitantly. A 15% decrease in the AUCτ,ssof pioglitazone with no alteration in Cmax,sswas observed. This finding was not statistically significant. In addition, a 13% and 16% decrease in Cmax,ssand AUCτ,ssrespectively, of the active hydroxy-metabolite was noted as well as a 60% decrease in Cmax,ssand AUCτ,ssof the active keto-metabolite. The clinical significance of these findings is not known.

Glyburide

A drug-drug interaction study conducted in patients with type 2 diabetes evaluated the steady-state pharmacokinetics of glyburide (5 mg/day) alone and concomitantly with topiramate (150 mg/day). There was a 22% decrease in Cmaxand a 25% reduction in AUC24for glyburide during topiramate administration. Systemic exposure (AUC) of the active metabolites, 4- trans-hydroxy-glyburide (M1) and 3- cis-hydroxyglyburide (M2), was also reduced by 13% and 15%, and Cmaxwas reduced by 18% and 25%, respectively. The steady-state pharmacokinetics of topiramate were unaffected by concomitant administration of glyburide.

Lithium

In patients, the pharmacokinetics of lithium were unaffected during treatment with topiramate at doses of 200 mg/day; however, there was an observed increase in systemic exposure of lithium (27% for Cmaxand 26% for AUC) following topiramate doses up to 600 mg/day [see Drug Interactions (7.7)] .

Haloperidol

The pharmacokinetics of a single dose of haloperidol (5 mg) were not affected following multiple dosing of topiramate (100 mg every 12 hr) in 13 healthy adults (6 males, 7 females).

Amitriptyline

There was a 12% increase in AUC and Cmaxfor amitriptyline (25 mg per day) in 18 healthy subjects (9 males, 9 females) receiving 200 mg/day of TOPAMAX.

Sumatriptan

Multiple dosing of topiramate (100 mg every 12 hours) in 24 healthy volunteers (14 males, 10 females) did not affect the pharmacokinetics of single-dose sumatriptan either orally (100 mg) or subcutaneously (6 mg).

Risperidone

When administered concomitantly with topiramate at escalating doses of 100, 250, and 400 mg/day, there was a reduction in risperidone systemic exposure (16% and 33% for steady-state AUC at the 250 and 400 mg/day doses of topiramate). No alterations of 9-hydroxyrisperidone levels were observed. Co-administration of topiramate 400 mg/day with risperidone resulted in a 14% increase in Cmaxand a 12% increase in AUC12of topiramate. There were no clinically significant changes in the systemic exposure of risperidone plus 9-hydroxyrisperidone or of topiramate; therefore, this interaction is not likely to be of clinical significance.

Propranolol

Multiple dosing of topiramate (200 mg/day) in 34 healthy volunteers (17 males, 17 females) did not affect the pharmacokinetics of propranolol following daily 160 mg doses. Propranolol doses of 160 mg/day in 39 volunteers (27 males, 12 females) had no effect on the exposure to topiramate, at a dose of 200 mg/day of topiramate.

Dihydroergotamine

Multiple dosing of topiramate (200 mg/day) in 24 healthy volunteers (12 males, 12 females) did not affect the pharmacokinetics of a 1 mg subcutaneous dose of dihydroergotamine. Similarly, a 1 mg subcutaneous dose of dihydroergotamine did not affect the pharmacokinetics of a 200 mg/day dose of topiramate in the same study.

Diltiazem

Co-administration of diltiazem (240 mg Cardizem CD) with topiramate (150 mg/day) resulted in a 10% decrease in Cmaxand a 25% decrease in diltiazem AUC, a 27% decrease in Cmaxand an 18% decrease in des-acetyl diltiazem AUC, and no effect on N-desmethyl diltiazem. Co-administration of topiramate with diltiazem resulted in a 16% increase in Cmaxand a 19% increase in AUC12of topiramate.

Venlafaxine

Multiple dosing of TOPAMAX (150 mg/day) in healthy volunteers did not affect the pharmacokinetics of venlafaxine or O-desmethyl venlafaxine. Multiple dosing of venlafaxine (150 mg) did not affect the pharmacokinetics of topiramate.

13 NON-CLINICAL TOXICOLOGY

13.1 Carcinogenesis, Mutagenesis, Impairment of Fertility

Carcinogenesis

An increase in urinary bladder tumors was observed in mice given topiramate (0, 20, 75, and 300 mg/kg/day) in the diet for 21 months. The increase in the incidence of bladder tumors in males and females receiving 300 mg/kg/day was primarily due to the increased occurrence of a smooth muscle tumor considered histomorphologically unique to mice. The higher of the doses not associated with an increase in tumors (75 mg/kg/day) is equivalent to the maximum recommended human dose (MRHD) for epilepsy (400 mg), and approximately 4 times the MRHD for migraine (100 mg) on a mg/m^2basis. The relevance of this finding to human carcinogenic risk is uncertain. No evidence of carcinogenicity was seen in rats following oral administration of topiramate for 2 years at doses up to 120 mg/kg/day (approximately 3 times the MRHD for epilepsy and 12 times the MRHD for migraine on a mg/m^2basis).

Mutagenesis

Topiramate did not demonstrate genotoxic potential when tested in a battery of in vitroand in vivoassays. Topiramate was not mutagenic in the Ames test or the in vitromouse lymphoma assay; it did not increase unscheduled DNA synthesis in rat hepatocytes in vitro; and it did not increase chromosomal aberrations in human lymphocytes in vitroor in rat bone marrow in vivo.

Impairment of Fertility

No adverse effects on male or female fertility were observed in rats administered topiramate orally at doses up to 100 mg/kg/day (2.5 times the MRHD for epilepsy and 10 times the MRHD for migraine on a mg/m^2basis) prior to and during mating and early pregnancy.

14 CLINICAL STUDIES

The studies described in the following sections were conducted using TOPAMAX (topiramate) Tablets.

14.1 Monotherapy Epilepsy

Patients with Partial-Onset or Primary Generalized Tonic-Clonic Seizures

Adults and Pediatric Patients 10 Years of Age and Older

The effectiveness of TOPAMAX as initial monotherapy in adults and pediatric patients 10 years of age and older with partial-onset or primary generalized tonic-clonic seizures was established in a multicenter, randomized, double-blind, parallel-group trial (Study 1).

Study 1 was conducted in 487 patients diagnosed with epilepsy (6 to 83 years of age) who had 1 or 2 well-documented seizures during the 3-month retrospective baseline phase who then entered the study and received TOPAMAX 25 mg/day for 7 days in an open-label fashion. Forty-nine percent of patients had no prior AED treatment and 17% had a diagnosis of epilepsy for greater than 24 months. Any AED therapy used for temporary or emergency purposes was discontinued prior to randomization. In the double-blind phase, 470 patients were randomized to titrate up to 50 mg/day or 400 mg/day. If the target dose could not be achieved, patients were maintained on the maximum tolerated dose. Fifty-eight percent of patients achieved the maximal dose of 400 mg/day for >2 weeks, and patients who did not tolerate 150 mg/day were discontinued.

The primary efficacy assessment was a between-group comparison of time to first seizure during the double-blind phase. Comparison of the Kaplan-Meier survival curves of time to first seizure favored the TOPAMAX 400 mg/day group over the TOPAMAX 50 mg/day group (Figure 1). The treatment effects with respect to time to first seizure were consistent across various patient subgroups defined by age, sex, geographic region, baseline body weight, baseline seizure type, time since diagnosis, and baseline AED use.

Figure 1: Kaplan-Meier Estimates of Cumulative Rates for Time to First Seizure in Study 1

Pediatric Patients 2 to 9 Years of Age

The conclusion that TOPAMAX is effective as initial monotherapy in pediatric patients 2 to 9 years of age with partial-onset or primary generalized tonic-clonic seizures was based on a pharmacometric bridging approach using data from the controlled epilepsy trials described in labeling. This approach consisted of first showing a similar exposure response relationship between pediatric patients down to 2 years of age and adults when TOPAMAX was given as adjunctive therapy. Similarity of exposure-response was also demonstrated in pediatric patients 6 to less than 16 years of age and adults when TOPAMAX was given as initial monotherapy. Specific dosing in pediatric patients 2 to 9 years of age was derived from simulations utilizing plasma exposure ranges observed in pediatric and adult patients treated with TOPAMAX initial monotherapy [see Dosage and Administration (2.1)] .

14.2 Adjunctive Therapy Epilepsy

Adult Patients With Partial-Onset Seizures

The effectiveness of TOPAMAX as an adjunctive treatment for adults with partial-onset seizures was established in six multicenter, randomized, double-blind, placebo-controlled trials (Studies 2, 3, 4, 5, 6, and 7), two comparing several dosages of TOPAMAX and placebo and four comparing a single dosage with placebo, in patients with a history of partial-onset seizures, with or without secondarily generalized seizures.

Patients in these studies were permitted a maximum of two antiepileptic drugs (AEDs) in addition to TOPAMAX tablets or placebo. In each study, patients were stabilized on optimum dosages of their concomitant AEDs during baseline phase lasting between 4 and 12 weeks. Patients who experienced a pre-specified minimum number of partial-onset seizures, with or without secondary generalization, during the baseline phase (12 seizures for 12-week baseline, 8 for 8-week baseline or 3 for 4-week baseline) were randomly assigned to placebo or a specified dose of TOPAMAX tablets in addition to their other AEDs.

Following randomization, patients began the double-blind phase of treatment. In five of the six studies, patients received active drug beginning at 100 mg per day; the dose was then increased by 100 mg or 200 mg/day increments weekly or every other week until the assigned dose was reached, unless intolerance prevented increases. In the sixth study (Study 7), the 25 or 50 mg/day initial doses of topiramate were followed by respective weekly increments of 25 or 50 mg/day until the target dose of 200 mg/day was reached. After titration, patients entered a 4, 8 or 12-week stabilization period. The numbers of patients randomized to each dose and the actual mean and median doses in the stabilization period are shown in Table 12.

Pediatric Patients 2 to 16 Years of Age with Partial-Onset Seizures

The effectiveness of TOPAMAX as an adjunctive treatment for pediatric patients 2 to 16 years of age with partial-onset seizures was established in a multicenter, randomized, double-blind, placebo-controlled trial (Study 8), comparing TOPAMAX and placebo in patients with a history of partial-onset seizures, with or without secondarily generalized seizures (see Table 13).

Patients in this study were permitted a maximum of two antiepileptic drugs (AEDs) in addition to TOPAMAX tablets or placebo. In this study, patients were stabilized on optimum dosages of their concomitant AEDs during an 8-week baseline phase. Patients who experienced at least six partial-onset seizures, with or without secondarily generalized seizures, during the baseline phase were randomly assigned to placebo or TOPAMAX tablets in addition to their other AEDs.

Following randomization, patients began the double-blind phase of treatment. Patients received active drug beginning at 25 or 50 mg/day; the dose was then increased by 25 mg to 150 mg/day increments every other week until the assigned dosage of 125, 175, 225, or 400 mg/day based on patients' weight to approximate a dosage of 6 mg/kg/day was reached, unless intolerance prevented increases. After titration, patients entered an 8-week stabilization period.

Patients With Primary Generalized Tonic-Clonic Seizures

The effectiveness of TOPAMAX as an adjunctive treatment for primary generalized tonic-clonic seizures in patients 2 years of age and older was established in a multicenter, randomized, double-blind, placebo-controlled trial (Study 9), comparing a single dosage of TOPAMAX and placebo (see Table 13).

Patients in Study 9 were permitted a maximum of two antiepileptic drugs (AEDs) in addition to TOPAMAX or placebo. Patients were stabilized on optimum dosages of their concomitant AEDs during an 8-week baseline phase. Patients who experienced at least three primary generalized tonic-clonic seizures during the baseline phase were randomly assigned to placebo or TOPAMAX in addition to their other AEDs.

Following randomization, patients began the double-blind phase of treatment. Patients received active drug beginning at 50 mg/day for four weeks; the dose was then increased by 50 mg to 150 mg/day increments every other week until the assigned dose of 175, 225, or 400 mg/day based on patients' body weight to approximate a dosage of 6 mg/kg/day was reached, unless intolerance prevented increases. After titration, patients entered a 12-week stabilization period.

Patients With Lennox-Gastaut Syndrome

The effectiveness of TOPAMAX as an adjunctive treatment for seizures associated with Lennox-Gastaut syndrome was established in a multicenter, randomized, double-blind, placebo-controlled trial (Study 10) comparing a single dosage of TOPAMAX with placebo in patients 2 years of age and older (see Table 13).

Patients in Study 10 were permitted a maximum of two antiepileptic drugs (AEDs) in addition to TOPAMAX or placebo. Patients who were experiencing at least 60 seizures per month before study entry were stabilized on optimum dosages of their concomitant AEDs during a 4-week baseline phase. Following baseline, patients were randomly assigned to placebo or TOPAMAX in addition to their other AEDs. Active drug was titrated beginning at 1 mg/kg/day for a week; the dose was then increased to 3 mg/kg/day for one week, then to 6 mg/kg/day. After titration, patients entered an 8-week stabilization period.

The primary measures of effectiveness were the percent reduction in drop attacks and a parental global rating of seizure severity.

Table 12: TOPAMAX Dose Summary During the Stabilization Periods of Each of Six Double-Blind, Placebo-Controlled, Adjunctive Trials in Adults with Partial-Onset Seizures [Dose-response studies were not conducted for other indications or pediatric partial-onset seizures.]
 |  |  | Target TOPAMAX Dosage (mg/day)
Study | Stabilization Dose | Placebo [Placebo dosages are given as the number of tablets. Placebo target dosages were as follows: Protocol 3 4 tablets/day; Protocols 1 and 4, 6 tablets/day; Protocols 5 and 6, 8 tablets/day; Protocol 2, 10 tablets/day.] | 200 | 400 | 600 | 800 | 1,000
2 | N | 42 | 42 | 40 | 41 | -- | --
 | Mean Dose | 5.9 | 200 | 390 | 556 | -- | --
 | Median Dose | 6.0 | 200 | 400 | 600 | -- | --
3 | N | 44 | -- | -- | 40 | 45 | 40
 | Mean Dose | 9.7 | -- | -- | 544 | 739 | 796
 | Median Dose | 10.0 | -- | -- | 600 | 800 | 1,000
4 | N | 23 | -- | 19 | -- | -- | --
 | Mean Dose | 3.8 | -- | 395 | -- | -- | --
 | Median Dose | 4.0 | -- | 400 | -- | -- | --
5 | N | 30 | -- | -- | 28 | -- | --
 | Mean Dose | 5.7 | -- | -- | 522 | -- | --
 | Median Dose | 6.0 | -- | -- | 600 | -- | --
6 | N | 28 | -- | -- | -- | 25 | --
 | Mean Dose | 7.9 | -- | -- | -- | 568 | --
 | Median Dose | 8.0 | -- | -- | -- | 600 | --
7 | N | 90 | 157 | -- | -- | -- | --
 | Mean Dose | 8 | 200 | -- | -- | -- | --
 | Median Dose | 8 | 200 | -- | -- | -- | --

In all adjunctive trials, the reduction in seizure rate from baseline during the entire double-blind phase was measured. The median percent reductions in seizure rates and the responder rates (fraction of patients with at least a 50% reduction) by treatment group for each study are shown below in Table 13. As described above, a global improvement in seizure severity was also assessed in the Lennox-Gastaut trial.

Table 13: Efficacy Results in Double-Blind, Placebo-Controlled, Adjunctive Epilepsy Trials
Target TOPAMAX Dosage (mg per day)
Study # | # | Placebo | 200 | 400 | 600 | 800 | 1,000 | ≈6 mg/kg/day [For Studies 8 and 9, specified target dosages (<9.3 mg/kg/day) were assigned based on subject's weight to approximate a dosage of 6 mg/kg per day; these dosages corresponded to mg/day dosages of 125, 175, 225, and 400 mg/day]
Partial-Onset Seizures Studies in Adults
2 | N | 45 | 45 | 45 | 46 | -- | -- | --
2 | Median % Reduction | 12 | 27a | 48b | 45c | -- | -- | --
2 | % Responders | 18 | 24 | 44d | 46d | -- | -- | --
3 | N | 47 | -- | -- | 48 | 48 | 47 | --
3 | Median % Reduction | 2 | -- | -- | 41c | 41c | 36c
3 | % Responders | 9 | -- | -- | 40c | 41c | 36d
4 | N | 24 | -- | 23 | -- | -- | -- | --
4 | Median % Reduction | 1 | -- | 41e | -- | -- | -- | --
4 | % Responders | 8 | -- | 35d | -- | -- | -- | --
5 | N | 30 | -- | -- | 30 | -- | -- | --
5 | Median % Reduction | -12 | -- | -- | 46f | -- | -- | --
5 | % Responders | 10 | -- | -- | 47c | -- | -- | --
6 | N | 28 | -- | -- | -- | 28 | -- | --
6 | Median % Reduction | -21 | -- | -- | -- | 24c | -- | --
6 | % Responders | 0 | -- | -- | -- | 43c | -- | --
7 | N | 91 | 168 | -- | -- | -- | -- | --
7 | Median % Reduction | 20 | 44c | -- | -- | -- | -- | --
7 | % Responders | 24 | 45c
Partial-Onset Seizures Studies in Pediatric Patients
8 | N | 45 | -- | -- | -- | -- | -- | 41
8 | Median % Reduction | 11 | -- | -- | -- | -- | -- | 33d
8 | % Responders | 20 | -- | -- | -- | -- | -- | 39
Primary Generalized Tonic-Clonich
9 | N | 40 | -- | -- | -- | -- | -- | 39
9 | Median % Reduction | 9 | -- | -- | -- | -- | -- | 57d
9 | % Responders | 20 | -- | -- | -- | -- | -- | 56c
Lennox-Gastaut Syndromei
10 | N | 49 | -- | -- | -- | -- | -- | 46
10 | Median % Reduction | -5 | -- | -- | -- | -- | -- | 15d
10 | % Responders | 14 |  |  |  |  |  | 28g
10 | Improvement in Seizure Severityj | 28 |  |  |  |  |  | 52d
Comparisons with placebo:ap=0.080;bp ≤ 0.010;cp ≤ 0.001;dp ≤ 0.050;ep=0.065;fp ≤0.005;gp=0.071;
hMedian % reduction and % responders are reported for PGTC seizures;
iMedian % reduction and % responders for drop attacks, i.e., tonic or atonic seizures
jPercentage of subjects who were minimally, much, or very much improved from baseline.

Subset analyses of the antiepileptic efficacy of TOPAMAX tablets in these studies showed no differences as a function of gender, race, age, baseline seizure rate, or concomitant AED.

In clinical trials for epilepsy, daily dosages were decreased in weekly intervals by 50 to 100 mg/day in adults and over a 2- to 8-week period in pediatric patients; transition was permitted to a new antiepileptic regimen when clinically indicated.

14.3 Preventive Treatment of Migraine

Adult Patients

The results of 2 multicenter, randomized, double-blind, placebo-controlled, parallel-group clinical trials established the effectiveness of TOPAMAX in the preventive treatment of migraine. The design of both trials (Study 11 was conducted in the U.S. and Study 12 was conducted in the U.S. and Canada) was identical, enrolling patients with a history of migraine, with or without aura, for at least 6 months, according to the International Headache Society (IHS) diagnostic criteria. Patients with a history of cluster headaches or basilar, ophthalmoplegic, hemiplegic, or transformed migraine headaches were excluded from the trials. Patients were required to have completed up to a 2-week washout of any prior migraine preventive medications before starting the baseline phase.

Patients who experienced 3 to 12 migraine headaches over the 4 weeks in the baseline phase were randomized to either TOPAMAX 50 mg/day, 100 mg/day, 200 mg/day, or placebo and treated for a total of 26 weeks (8-week titration period and 18-week maintenance period). Treatment was initiated at 25 mg/day for one week, and then the daily dosage was increased by 25 mg increments each week until reaching the assigned target dose or maximum tolerated dose (administered twice daily).

Effectiveness of treatment was assessed by the reduction in migraine headache frequency, as measured by the change in 4-week migraine rate (according to migraines classified by IHS criteria) from the baseline phase to double-blind treatment period in each TOPAMAX treatment group compared to placebo in the Intent-To-Treat (ITT) population.

In Study 11, a total of 469 patients (416 females, 53 males), ranging in age from 13 to 70 years, were randomized and provided efficacy data. Two hundred sixty-five patients completed the entire 26-week double-blind phase. The median average daily dosages were 48 mg/day, 88 mg/day, and 132 mg/day in the target dose groups of TOPAMAX 50, 100, and 200 mg/day, respectively.

The mean migraine headache frequency rate at baseline was approximately 5.5 migraine headaches/28 days and was similar across treatment groups. The change in the mean 4-week migraine headache frequency from baseline to the double-blind phase was -1.3, -2.1, and -2.2 in the TOPAMAX 50, 100, and 200 mg/day groups, respectively, versus -0.8 in the placebo group (see Figure 2). The treatment differences between the TOPAMAX 100 and 200 mg/day groups versus placebo were similar and statistically significant (p<0.001 for both comparisons).

In Study 12, a total of 468 patients (406 females, 62 males), ranging in age from 12 to 65 years, were randomized and provided efficacy data. Two hundred fifty-five patients completed the entire 26-week double-blind phase. The median average daily dosages were 47 mg/day, 86 mg/day, and 150 mg/day in the target dose groups of TOPAMAX 50, 100, and 200 mg/day, respectively.

The mean migraine headache frequency rate at baseline was approximately 5.5 migraine headaches/28 days and was similar across treatment groups. The change in the mean 4-week migraine headache period frequency from baseline to the double-blind phase was -1.4, -2.1, and -2.4 in the TOPAMAX 50, 100, and 200 mg/day groups, respectively, versus -1.1 in the placebo group (see Figure 2). The differences between the TOPAMAX 100 and 200 mg/day groups versus placebo were similar and statistically significant (p=0.008 and p <0.001, respectively).

In both studies, there were no apparent differences in treatment effect within age or gender subgroups. Because most patients were Caucasian, there were insufficient numbers of patients from different races to make a meaningful comparison of race.

For patients withdrawing from TOPAMAX, daily dosages were decreased in weekly intervals by 25 to 50 mg/day.

Figure 2: Reduction in 4-Week Migraine Headache Frequency

(Studies 11 and 12 for Adults and Adolescents)

Pediatric Patients 12 to 17 Years of Age

The effectiveness of TOPAMAX for the preventive treatment of migraine in pediatric patients 12 to 17 years of age was established in a multicenter, randomized, double-blind, parallel-group trial (Study 13). The study enrolled 103 patients (40 male, 63 female) 12 to 17 years of age with episodic migraine headaches with or without aura. Patient selection was based on IHS criteria for migraines (using proposed revisions to the 1988 IHS pediatric migraine criteria [IHS-R criteria]).

Patients who experienced 3 to 12 migraine attacks (according to migraines classified by patient reported diaries) and ≤14 headache days (migraine and non-migraine) during the 4-week prospective baseline period were randomized to either TOPAMAX 50 mg/day, 100 mg/day, or placebo and treated for a total of 16 weeks (4-week titration period followed by a 12-week maintenance period). Treatment was initiated at 25 mg/day for one week, and then the daily dosage was increased by 25 mg increments each week until reaching the assigned target dose or maximum tolerated dose (administered twice daily). Approximately 80% or more patients in each treatment group completed the study. The median average daily dosages were 45 and 79 mg/day in the target dose groups of TOPAMAX 50 and 100 mg/day, respectively.

Effectiveness of treatment was assessed by comparing each TOPAMAX treatment group to placebo (ITT population) for the percent reduction from baseline to the last 12 weeks of the double-blind phase in the monthly migraine attack rate (primary endpoint). The percent reduction from baseline to the last 12 weeks of the double-blind phase in average monthly migraine attack rate is shown in Table 14. The 100 mg TOPAMAX dose produced a statistically significant treatment difference relative to placebo of 28% reduction from baseline in the monthly migraine attack rate.

The mean reduction from baseline to the last 12 weeks of the double-blind phase in average monthly attack rate, a key secondary efficacy endpoint in Study 13 (and the primary efficacy endpoint in Studies 11 and 12, of adults) was 3.0 for 100 mg TOPAMAX dose and 1.7 for placebo. This 1.3 treatment difference in mean reduction from baseline of monthly migraine rate was statistically significant (p = 0.0087).

Table 14: Percent Reduction from Baseline to the Last 12 Weeks of Double-Blind Phase in Average Monthly Attack Rate: Study 13 (Intent-to-Treat Analysis Set)
 | Placebo | TOPAMAX 50 mg/day | TOPAMAX 100 mg/day
Category | (N=33) | (N=35) | (N=35)
Baseline
Median | 3.6 | 4.0 | 4.0
Last 12 Weeks of Double-Blind Phase
Median | 2.3 | 2.3 | 1.0
Percent Reduction (%)
Median | 44.4 | 44.6 | 72.2
P-value versus Placebo [P-values (two-sided) for comparisons relative to placebo are generated by applying an ANCOVA model on ranks that includes subject's stratified age at baseline, treatment group, and analysis center as factors and monthly migraine attack rate during baseline period as a covariate.] , [P-values for the dose groups are the adjusted p-value according to the Hochberg multiple comparison procedure.] |  | 0.7975 | 0.0164 [Indicates p-value is <0.05 (two-sided).]

16 HOW SUPPLIED/STORAGE AND HANDLING

16.1 How Supplied

TOPAMAX Tablets

TOPAMAX®(topiramate) Tablets are available as debossed, coated, round tablets in the following strengths and colors:

- 25 mg cream tablet (debossed "OMN" on one side; "25" on the other) and are available in bottles of 60 count with desiccant (NDC 50458-639-65)
- 50 mg light yellow tablet (debossed "OMN" on one side; "50" on the other) and are available in bottles of 60 count with desiccant (NDC 50458-640-65)
- 100 mg yellow tablet (debossed "OMN" on one side; "100" on the other) and are available in bottles of 60 count with desiccant (NDC 50458-641-65)
- 200 mg salmon tablet (debossed "OMN" on one side; "200" on the other) and are available in bottles of 60 count with desiccant (NDC 50458-642-65)

TOPAMAX Sprinkle Capsules

TOPAMAX®(topiramate capsules) Sprinkle Capsules contain small, white to off-white spheres. The gelatin capsules are white and clear and are marked as follows:

- 15 mg capsule with "TOP" and "15 mg" on the side and are available in bottles of 60 (NDC 50458-647-65)
- 25 mg capsule with "TOP" and "25 mg" on the side and are available in bottles of 60 (NDC 50458-645-65)

16.2 Storage and Handling

TOPAMAX Tablets

TOPAMAX Tablets should be stored in tightly-closed containers at controlled room temperature (59 ° to 86 °F, 15 ° to 30 °C). Protect from moisture.

TOPAMAX Sprinkle Capsules

TOPAMAX Sprinkle Capsules should be stored in tightly-closed containers at or below 25 °C (77 °F). Protect from moisture.

17 PATIENT COUNSELING INFORMATION

Advise the patient to read the FDA-approved patient labeling (Medication Guide).

Eye Disorders

Instruct patients taking TOPAMAX to seek immediate medical attention if they experience blurred vision, visual disturbances, or periorbital pain [see Warnings and Precautions (5.1, 5.2)] .

Oligohidrosis and Hyperthermia

Closely monitor TOPAMAX-treated patients, especially pediatric patients, for evidence of decreased sweating and increased body temperature, especially in hot weather. Counsel patients to contact their healthcare professionals immediately if they develop a high or persistent fever, or decreased sweating [see Warnings and Precautions (5.3)] .

Metabolic Acidosis

Warn patients about the potential significant risk for metabolic acidosis that may be asymptomatic and may be associated with adverse effects on kidneys (e.g., kidney stones, nephrocalcinosis), bones (e.g., osteoporosis, osteomalacia, and/or rickets in children), and growth (e.g., growth delay/retardation) in pediatric patients, and on the fetus [see Warnings and Precautions (5.4), Use in Specific Populations (8.1)] .

Suicidal Behavior and Ideation

Counsel patients, their caregivers, and families that AEDs, including TOPAMAX, may increase the risk of suicidal thoughts and behavior, and advise of the need to be alert for the emergence or worsening of the signs and symptoms of depression, any unusual changes in mood or behavior or the emergence of suicidal thoughts, or behavior or thoughts about self-harm. Instruct patients to immediately report behaviors of concern to their healthcare providers [see Warnings and Precautions (5.5)] .

Interference with Cognitive and Motor Performance

Warn patients about the potential for somnolence, dizziness, confusion, difficulty concentrating, or visual effects, and advise patients not to drive or operate machinery until they have gained sufficient experience on TOPAMAX to gauge whether it adversely affects their mental performance, motor performance, and/or vision [see Warnings and Precautions (5.6)] .

Even when taking TOPAMAX or other anticonvulsants, some patients with epilepsy will continue to have unpredictable seizures. Therefore, advise all patients taking TOPAMAX for epilepsy to exercise appropriate caution when engaging in any activities where loss of consciousness could result in serious danger to themselves or those around them (including swimming, driving a car, climbing in high places, etc.). Some patients with refractory epilepsy will need to avoid such activities altogether. Discuss the appropriate level of caution with patients, before patients with epilepsy engage in such activities.

Fetal Toxicity

Inform pregnant women and women of childbearing potential that use of TOPAMAX during pregnancy can cause fetal harm. TOPAMAX increases the risk of major congenital malformations, including but not limited to cleft lip and/or cleft palate (oral clefts), which occur early in pregnancy before many women know they are pregnant. Also inform patients that infants exposed to topiramate monotherapy in uteromay be SGA [see Use in Specific Populations (8.1)] . There may also be risks to the fetus from chronic metabolic acidosis with use of TOPAMAX during pregnancy [see Warnings and Precautions (5.7), Use in Specific Populations (8.1)] . When appropriate, counsel pregnant women and women of childbearing potential about alternative therapeutic options.

Advise women of childbearing potential who are not planning a pregnancy to use effective contraception while using TOPAMAX, keeping in mind that there is a potential for decreased contraceptive efficacy when using estrogen-containing or progestin-only contraceptives with topiramate [see Drug Interactions (7.4)] .

Encourage pregnant women using TOPAMAX, to enroll in the North American Antiepileptic Drug (NAAED) Pregnancy Registry. The registry is collecting information about the safety of antiepileptic drugs during pregnancy [see Use in Specific Populations (8.1)] .

Decrease in Bone Mineral Density

Inform the patient or caregiver that long-term treatment with TOPAMAX can decrease bone formation and increase bone resorption in children [see Warnings and Precautions (5.9)].

Negative Effects on Growth (Height and Weight)

Discuss with the patient or caregiver that long-term TOPAMAX treatment may attenuate growth as reflected by slower height increase and weight gain in pediatric patients [see Warnings and Precautions (5.10)].

Serious Skin Reactions

Inform patients about the signs of serious skin reactions. Instruct patients to immediately inform their healthcare provider at the first appearance of skin rash [see Warnings and Precautions (5.11)] .

Hyperammonemia and Encephalopathy

Warn patients about the possible development of hyperammonemia with or without encephalopathy. Although hyperammonemia may be asymptomatic, clinical symptoms of hyperammonemic encephalopathy often include acute alterations in level of consciousness and/or cognitive function with lethargy and/or vomiting. This hyperammonemia and encephalopathy can develop with TOPAMAX treatment alone or with TOPAMAX treatment with concomitant valproic acid (VPA).

Instruct patients to contact their physician if they develop unexplained lethargy, vomiting, or changes in mental status [see Warnings and Precautions (5.12)].

Kidney Stones

Instruct patients, particularly those with predisposing factors, to maintain an adequate fluid intake in order to minimize the risk of kidney stone formation [see Warnings and Precautions (5.13)].

Instructions for a Missing Dose

Instruct patients that if they miss a single dose of TOPAMAX, it should be taken as soon as possible. However, if a patient is within 6 hours of taking the next scheduled dose, tell the patient to wait until then to take the usual dose of TOPAMAX, and to skip the missed dose. Tell patients that they should not take a double dose in the event of a missed dose. Advise patients to contact their healthcare provider if they have missed more than one dose.

Manufactured by:

Janssen Ortho LLC

Gurabo, Puerto Rico 00778

Manufactured for:

Janssen Pharmaceuticals, Inc.

Titusville, NJ 08560, USA

© Johnson & Johnson and its affiliates 2025

MEDICATION GUIDE
TOPAMAX®(TOE-PA-MAX)
(topiramate)
TABLETS, for oral use
TOPAMAX®(TOE-PA-MAX)
(topiramate capsules)
SPRINKLE CAPSULES, for oral use

What is the most important information I should know about TOPAMAX?
TOPAMAX may cause eye problems. Serious eye problems include:

- any sudden decrease in vision with or without eye pain and redness.
- a blockage of fluid in the eye causing increased pressure in the eye (secondary angle closure glaucoma).
- These eye problems can lead to permanent loss of vision if not treated.
- You should call your healthcare provider right away if you have any new eye symptoms, including any new problems with your vision.

TOPAMAX may cause decreased sweating and increased body temperature (fever).People, especially children, should be watched for signs of decreased sweating and fever, especially in hot temperatures. Some people may need to be hospitalized for this condition. If a high fever, a fever that does not go away, or decreased sweating develops, call your healthcare provider right away.
TOPAMAX can increase the level of acid in your blood (metabolic acidosis).If left untreated, metabolic acidosis can cause brittle or soft bones (osteoporosis, osteomalacia, osteopenia), kidney stones, can slow the rate of growth in children, and may possibly harm your baby if you are pregnant. Metabolic acidosis can happen with or without symptoms. Sometimes people with metabolic acidosis will:

- feel tired
- not feel hungry (loss of appetite)

- feel changes in heartbeat
- have trouble thinking clearly

Your healthcare provider should do a blood test to measure the level of acid in your blood before and during your treatment with TOPAMAX. If you are pregnant, you should talk to your healthcare provider about whether you have metabolic acidosis.
Like other antiepileptic drugs, TOPAMAX may cause suicidal thoughts or actions in a very small number of people, about 1 in 500.
Call a healthcare provider right away if you have any of these symptoms, especially if they are new, worse, or worry you:

- thoughts about suicide or dying
- attempts to commit suicide
- new or worse depression
- new or worse anxiety
- feeling agitated or restless
- panic attacks

- trouble sleeping (insomnia)
- new or worse irritability
- acting aggressive, being angry, or violent
- acting on dangerous impulses
- an extreme increase in activity and talking (mania)
- other unusual changes in behavior or mood

Do not stop TOPAMAX without first talking to a healthcare provider.

- Stopping TOPAMAX suddenly can cause serious problems.
- Suicidal thoughts or actions can be caused by things other than medicines. If you have suicidal thoughts or actions, your healthcare provider may check for other causes.

How can I watch for early symptoms of suicidal thoughts and actions?

- Pay attention to any changes, especially sudden changes, in mood, behaviors, thoughts, or feelings.
- Keep all follow-up visits with your healthcare provider as scheduled.
- Call your healthcare provider between visits as needed, especially if you are worried about symptoms.

TOPAMAX can harm your unborn baby.

- If you take TOPAMAX during pregnancy, your baby has a higher risk for birth defects including cleft lip and cleft palate. These defects can begin early in pregnancy, even before you know you are pregnant.
- Birth defects may happen even in children born to women who are not taking any medicines and do not have other risk factors.
- There may be other medicines to treat your condition that have a lower chance of birth defects.
- All women of childbearing age should talk to their healthcare providers about using other possible treatments instead of TOPAMAX. If the decision is made to use TOPAMAX, you should use effective birth control (contraception) unless you are planning to become pregnant. You should talk to your doctor about the best kind of birth control to use while you are taking TOPAMAX.
- Tell your healthcare provider right away if you become pregnant while taking TOPAMAX. You and your healthcare provider should decide if you will continue to take TOPAMAX while you are pregnant.
- If you take TOPAMAX during pregnancy, your baby may be smaller than expected at birth. The long-term effects of this are not known. Talk to your healthcare provider if you have questions about this risk during pregnancy.
- Metabolic acidosis may have harmful effects on your baby. Talk to your healthcare provider if TOPAMAX has caused metabolic acidosis during your pregnancy.
- Pregnancy Registry: If you become pregnant while taking TOPAMAX, talk to your healthcare provider about registering with the North American Antiepileptic Drug Pregnancy Registry. You can enroll in this registry by calling 1-888-233-2334. The purpose of this registry is to collect information about the safety of TOPAMAX and other antiepileptic drugs during pregnancy.

TOPAMAX may decrease the density of bones when used over a long period.
TOPAMAX may slow height increase and weight gain in children and adolescents when used over a long period.

What is TOPAMAX?
TOPAMAX is a prescription medicine used:

- to treat certain types of seizures (partial-onset seizures and primary generalized tonic-clonic seizures) in adults and children 2 years and older,
- with other medicines to treat certain types of seizures (partial-onset seizures, primary generalized tonic-clonic seizures, and seizures associated with Lennox-Gastaut syndrome) in adults and children 2 years and older,
- to prevent migraine headaches in adults and adolescents 12 years and older.

Before taking TOPAMAX, tell your healthcare provider about all of your medical conditions, including if you:

- have or have had depression, mood problems, or suicidal thoughts or behavior.
- have kidney problems, have kidney stones, or are getting kidney dialysis.
- have a history of metabolic acidosis (too much acid in the blood).
- have liver problems.
- have weak, brittle, or soft bones (osteomalacia, osteoporosis, osteopenia, or decreased bone density).
- have lung or breathing problems.
- have eye problems, especially glaucoma.
- have diarrhea.
- have a growth problem.
- are on a diet high in fat and low in carbohydrates, which is called a ketogenic diet.
- are having surgery.
- are pregnant or plan to become pregnant.
- are breastfeeding or plan to breastfeed. TOPAMAX passes into breast milk. Breastfed babies may be sleepy or have diarrhea. It is not known if the TOPAMAX that passes into breast milk can cause other serious harm to your baby. Talk to your healthcare provider about the best way to feed your baby if you take TOPAMAX.

Tell your healthcare provider about all the medicines you take, including prescription and over-the-counter medicines, vitamins, and herbal supplements. TOPAMAX and other medicines may affect each other causing side effects.
Especially tell your healthcare provider if you take:

- Valproic acid (such as DEPAKENE or DEPAKOTE).
- any medicines that impair or decrease your thinking, concentration, or muscle coordination.
- birth control that contains hormones (such as pills, implants, patches or injections). TOPAMAX may make your birth control less effective. Tell your healthcare provider if your menstrual bleeding changes while you are using birth control and TOPAMAX.

Ask your healthcare provider if you are not sure if your medicine is listed above.
Know the medicines you take. Keep a list of them to show your healthcare provider and pharmacist each time you get a new medicine. Do not start a new medicine without talking with your healthcare provider.

How should I take TOPAMAX?

- Take TOPAMAX exactly as prescribed.
- Your healthcare provider may change your dose. Do notchange your dose without talking to your healthcare provider.
- Take TOPAMAX Tablets whole. Do notchew the tablets. They may leave a bitter taste.
- TOPAMAX Sprinkle Capsules may be swallowed whole or may be opened and sprinkled on a teaspoon of soft food. Drink fluids right after eating the food and medicine mixture to make sure it is all swallowed. Do notchew the food and medicine mixture.
- Do notstore any medicine and food mixture for later use.
- TOPAMAX can be taken before, during, or after a meal. Drink plenty of fluids during the day. This may help prevent kidney stones while taking TOPAMAX.
- If you take too much TOPAMAX, call your healthcare provider right away or go to the nearest emergency room.
- If you miss a single dose of TOPAMAX, take it as soon as you can. However, if you are within 6 hours of taking your next scheduled dose, wait until then to take your usual dose of TOPAMAX, and skip the missed dose. Do notdouble your dose. If you have missed more than one dose, you should call your healthcare provider for advice.
- Do notstop taking TOPAMAX without talking to your healthcare provider. Stopping TOPAMAX suddenly may cause serious problems. If you have epilepsy and you stop taking TOPAMAX suddenly, you may have seizures that do not stop. Your healthcare provider will tell you how to stop taking TOPAMAX slowly.
- Your healthcare provider may do blood tests while you take TOPAMAX.

What should I avoid while taking TOPAMAX?

- You should not drink alcohol while taking TOPAMAX. TOPAMAX and alcohol can affect each other causing side effects such as sleepiness and dizziness.
- Do not drive a car or operate machinery until you know how TOPAMAX affects you. TOPAMAX can slow your thinking and motor skills, and may affect vision.

What are the possible side effects of TOPAMAX?
TOPAMAX may cause serious side effects including :
See " What is the most important information I should know about TOPAMAX?"

- High blood ammonia levels.High ammonia in the blood can affect your mental activities, slow your alertness, make you feel tired, or cause vomiting. This has happened when TOPAMAX is taken with a medicine called valproic acid (DEPAKENE and DEPAKOTE).
- Effects on thinking and alertness.TOPAMAX may affect how you think and cause confusion, problems with concentration, attention, memory, or speech. TOPAMAX may cause depression or mood problems, tiredness, and sleepiness.
- Dizziness or loss of muscle coordination.
- Serious skin reactions.TOPAMAX may cause a severe rash with blisters and peeling skin, especially around the mouth, nose, eyes, and genitals (Stevens-Johnson syndrome). TOPAMAX may also cause a rash with blisters and peeling skin over much of the body that may cause death (toxic epidermal necrolysis). Call your healthcare provider right away if you develop a skin rash or blisters.
- Kidney stones.Drink plenty of fluids when taking TOPAMAX to decrease your chances of getting kidney stones.
- Low body temperature.Taking TOPAMAX when you are also taking valproic acid can cause a drop in body temperature to less than 95 °F, or can cause tiredness, confusion, or coma.

Call your healthcare provider right away if you have any of the symptoms above.
The most common side effects of TOPAMAX include:

- tingling of the arms and legs (paresthesia)
- not feeling hungry
- nausea
- a change in the way foods taste
- diarrhea
- weight loss

- nervousness
- upper respiratory tract infection
- speech problems
- tiredness
- dizziness
- sleepiness/drowsiness

- slow reactions
- difficulty with memory
- pain in the abdomen
- fever
- abnormal vision
- decreased feeling or sensitivity, especially in the skin

Tell your healthcare provider about any side effect that bothers you or that does not go away. These are not all the possible side effects of TOPAMAX. Call your doctor for medical advice about side effects. You may report side effects to FDA at 1-800-FDA-1088. You may also report side effects to Janssen Pharmaceuticals, Inc. at 1-800-526-7736.

How should I store TOPAMAX?

- Store TOPAMAX Tablets at room temperature between 59 °F to 86 °F (15 °C to 30 °C).
- Store TOPAMAX Sprinkle Capsules at or below 77 °F (25 °C).
- Keep TOPAMAX in a tightly closed container.
- Keep TOPAMAX dry and away from moisture.

Keep TOPAMAX and all medicines out of the reach of children.

General information about the safe and effective use of TOPAMAX.
Medicines are sometimes prescribed for purposes other than those listed in a Medication Guide. Do not use TOPAMAX for a condition for which it was not prescribed. Do not give TOPAMAX to other people, even if they have the same symptoms that you have. It may harm them.
You can ask your pharmacist or healthcare provider for information about TOPAMAX that is written for health professionals.

What are the ingredients in TOPAMAX?
Active ingredient:topiramate
Inactive ingredients:

- Tablets -carnauba wax, hypromellose, lactose monohydrate, magnesium stearate, microcrystalline cellulose, polyethylene glycol, polysorbate 80, pregelatinized starch, purified water, sodium starch glycolate, synthetic iron oxide, and titanium dioxide.
- Sprinkle Capsules -black pharmaceutical ink, cellulose acetate, gelatin, povidone, sodium lauryl sulfate, sorbitan monolaurate, sugar spheres (sucrose and starch) and titanium dioxide.

Manufactured by: Janssen Ortho LLC, Gurabo, Puerto Rico 00778; Manufactured for: Janssen Pharmaceuticals, Inc., Titusville, NJ 08560, USA
© Johnson & Johnson and its affiliates 2025
For more information, go to www.topamax.com or call 1-800-526-7736.

This Medication Guide has been approved by the U.S. Food and Drug Administration

Revised: 3/2025

PRINCIPAL DISPLAY PANEL - 25 mg Tablet Bottle Label

NDC 50458-639-65

TopAMAX®
(topiramate) Tablets

25 mg

CAUTION: Verify Prescription Before Dispensing

Attention: Dispense the enclosed Medication
Guide to each patient.

Rx only
60 tablets

Johnson
&Johnson

PRINCIPAL DISPLAY PANEL - 50 mg Tablet Bottle Label

NDC 50458-640-65

TopAMAX®
(topiramate) Tablets

50 mg

CAUTION: Verify Prescription Before Dispensing

Attention: Dispense the enclosed Medication
Guide to each patient.

Rx only
60 tablets

Johnson
&Johnson

PRINCIPAL DISPLAY PANEL - 100 mg Tablet Bottle Label

NDC 50458-641-65

TopAMAX®
(topiramate) Tablets

100 mg

CAUTION: Verify Prescription Before Dispensing

Attention: Dispense the enclosed Medication
Guide to each patient.

Rx only
60 tablets

Johnson
&Johnson

PRINCIPAL DISPLAY PANEL - 200 mg Tablet Bottle Label

NDC 50458-642-65

TopAMAX®
(topiramate) Tablets

200 mg

CAUTION: Verify Prescription Before Dispensing

Attention: Dispense the enclosed Medication
Guide to each patient.

Rx only
60 tablets

Johnson
&Johnson

PRINCIPAL DISPLAY PANEL - 15 mg Capsule Bottle Label

NDC 50458-647-65
Rx only

TopAMAX®
(topiramate)
Sprinkle Capsules

15 mg

Attention: Dispense the enclosed Medication
Guide to each patient.

60 capsules

Johnson
&Johnson

PRINCIPAL DISPLAY PANEL - 25 mg Capsule Bottle Label

NDC 50458-645-65
Rx only

TopAMAX®
(topiramate)
Sprinkle Capsules

25 mg

Attention: Dispense the enclosed Medication
Guide to each patient.

60 capsules

Johnson
&Johnson